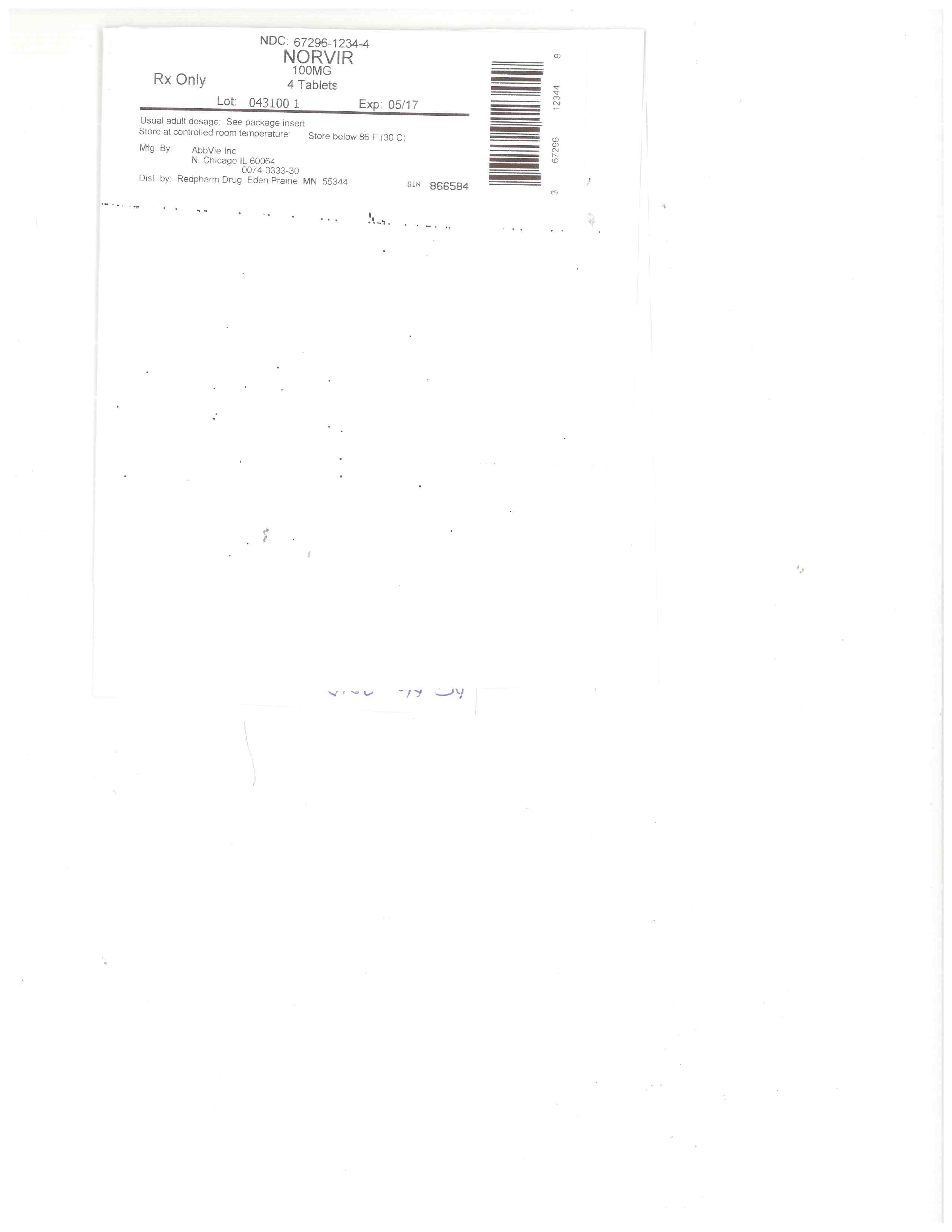 DRUG LABEL: Norvir
NDC: 67296-1234 | Form: TABLET, FILM COATED
Manufacturer: RedPharm Drug, Inc.
Category: prescription | Type: HUMAN PRESCRIPTION DRUG LABEL
Date: 20200120

ACTIVE INGREDIENTS: RITONAVIR 100 mg/1 1
INACTIVE INGREDIENTS: ANHYDROUS DIBASIC CALCIUM PHOSPHATE; TITANIUM DIOXIDE; POLYETHYLENE GLYCOL 3350; SILICON DIOXIDE; SORBITAN MONOLAURATE; SODIUM STEARYL FUMARATE; POLYETHYLENE GLYCOL 400; POLYSORBATE 80; HYPROMELLOSES; HYDROXYPROPYL CELLULOSE (1600000 WAMW); COPOVIDONE K25-31; TALC

BOXED WARNIING

WARNING: DRUG-DRUG INTERACTIONS LEADING TO POTENTIALLY SERIOUS AND/OR LIFE THREATENING REACTIONS

Co-administration of NORVIR with several classes of drugs including sedative hypnotics, antiarrhythmics, or ergot alkaloid preparations may result in potentially serious and/or life-threatening adverse events due to possible effects of NORVIR on the hepatic metabolism of certain drugs. Review medications taken by patients prior to prescribing NORVIR or when prescribing other medications to patients already taking NORVIR [see Contraindications (4), Warnings and Precautions (5.1), Drug Interactions (7), and Clinical Pharmacology (12.3)].

HIGHLIGHTS OF PRESCRIBING INFORMATION

These highlights do not include all the information needed to use NORVIR safely and effectively. See full prescribing information for NORVIR.
NORVIR (ritonavir) tablet, for oral use
NORVIR (ritonavir) solution, for oral use
Initial U.S. Approval: 1996

WARNING: DRUG-DRUG INTERACTIONS LEADING TO POTENTIALLY SERIOUS AND/OR LIFE THREATENING REACTIONS
SEE FULL PRESCRIBING INFORMATION FOR COMPLETE BOXED WARNING

Co-administration of NORVIR with several classes of drugs including sedative hypnotics, antiarrhythmics, or ergot alkaloid preparations may result in potentially serious and/or life-threatening adverse events due to possible effects of NORVIR on the hepatic metabolism of certain drugs. Review medications taken by patients prior to prescribing NORVIR or when prescribing other medications to patients already taking NORVIR [see Contraindications (4), Warnings and Precautions (5.1), Drug Interactions (7), and Clinical Pharmacology (12.3)].

RECENT MAJOR CHANGES

Dosage and Administration (2.1) 12/2016
Contraindications (4) 11/2016
Warnings and Precautions
Diabetes Mellitus/Hyperglycemia (5.8) 11/2016

INDICATIONS AND USAGE

NORVIR is an HIV protease inhibitor indicated in combination with other antiretroviral agents for the treatment of HIV-1 infection (1)

DOSAGE AND ADMINISTRATION

Dose modification for NORVIR is necessary when used with other protease inhibitors (2)
Adult patients: 600 mg twice-day with meals (2.1)
Pediatrics patients: The recommended twice daily dose for children greater than one month of age is based on body surface area and should not exceed 600 mg twice daily with meals (2.2)
NORVIR oral solution should not be administered to neonates before a postmenstrual age (first day of the mother’s last menstrual period to birth plus the time elapsed after birth) of 44 weeks has been attained (2.2, 5.2)

DOSAGE FORMS AND STRENGTHS

Tablet: 100 mg ritonavir (3)
Oral solution: 80 mg ritonavir per milliliter (3)

CONTRAINDICATIONS

NORVIR is contraindicated in patients with known hypersensitivity to ritonavir (e.g., toxic epidermal necrolysis, Stevens-Johnson syndrome) or any of its ingredients (4)
Co-administration with drugs highly dependent on CYP3A for clearance and for which elevated plasma concentrations may be associated with serious and/or life-threatening events (4)
Co-administration with drugs that significantly reduce ritonavir (4)

WARNINGS AND PRECAUTIONS

The following have been observed in patients receiving NORVIR:

The concomitant use of NORVIR and certain other drugs may result in known or potentially significant drug interactions. Consult the full prescribing information prior to and during treatment for potential drug interactions. (5.1, 7.2)
Toxicity in preterm neonates: NORVIR oral solution should not be used in preterm neonates in the immediate postnatal period because of possible toxicities. A safe and effective dose of NORVIR oral solution in this patient population has not been established (2.2,5.2)
Hepatic Reactions: Fatalities have occurred. Monitor liver function before and during therapy, especially in patients with underlying hepatic disease, including hepatitis B and hepatitis C, or marked transaminase elevations (5.3, 8.6)
Pancreatitis: Fatalities have occurred; suspend therapy as clinically appropriate (5.4)
Allergic Reactions/Hypersensitivity: Allergic reactions have been reported and include anaphylaxis, toxic epidermal necrolysis, Stevens-Johnson syndrome, bronchospasm and angioedema. Discontinue treatment if severe reactions develop (5.5, 6.2)
PR interval prolongation may occur in some patients. Cases of second and third degree heart block have been reported. Use with caution with patients with preexisting conduction system disease, ischemic heart disease, cardiomyopathy, underlying structural heart disease or when administering with other drugs that may prolong the PR interval (5.6, 12.3)
Total cholesterol and triglycerides elevations: Monitor prior to therapy and periodically thereafter (5.7)
Patients may develop new onset or exacerbations of diabetes mellitus, hyperglycemia (5.8)
Patients may develop immune reconstitution syndrome (5.9)
Patients may develop redistribution/accumulation of body fat (5.10)
Hemophilia: Spontaneous bleeding may occur, and additional factor VIII may be required (5.11)

ADVERSE REACTIONS

The most frequently reported adverse drug reactions among patients receiving NORVIR alone or in combination with other antiretroviral drugs were gastrointestinal (including diarrhea, nausea, vomiting, abdominal pain (upper and lower), neurological disturbances (including paresthesia and oral paresthesia), rash, and fatigue/asthenia (6.1)

To report SUSPECTED ADVERSE REACTIONS, contact AbbVie Inc. at 1-800-633-9110 or FDA at 1-800-FDA-1088 or www.fda.gov/medwatch.

DRUG INTERACTIONS

Co-administration of NORVIR can alter the concentrations of other drugs. The potential for drug-drug interactions must be considered prior to and during therapy (4, 5.1, 7, 12.3)

USE IN SPECIFIC POPULATIONS

Lactation: Women infected with HIV should be instructed not to breastfeed due to the potential for HIV transmission (8.2).

See 17 for PATIENT COUNSELING INFORMATION and FDA-approved patient labeling.

Revised: 12/2016

FULL PRESCRIBING INFORMATION: CONTENTS*

WARNING: DRUG-DRUG INTERACTIONS LEADING TO POTENTIALLY SERIOUS AND/OR LIFE THREATENING REACTIONS
1 INDICATIONS AND USAGE
2 DOSAGE AND ADMINISTRATION
2.1 Adult Patients
2.2 Pediatric Patients
3 DOSAGE FORMS AND STRENGTHS
4 CONTRAINDICATIONS
5 WARNINGS AND PRECAUTIONS
5.1 Risk of Serious Adverse Reactions Due to Drug Interactions
5.2 Toxicity in Preterm Neonates
5.3 Hepatic Reactions
5.4 Pancreatitis
5.5 Allergic Reactions/Hypersensitivity
5.6 PR Interval Prolongation
5.7 Lipid Disorders
5.8 Diabetes Mellitus/Hyperglycemia
5.9 Immune Reconstitution Syndrome
5.10 Fat Redistribution
5.11 Patients with Hemophilia
5.12 Resistance/Cross-resistance
5.13 Laboratory Tests
6 ADVERSE REACTIONS
6.1 Clinical Trial Experience
6.2 Postmarketing Experience
7 DRUG INTERACTIONS
7.1 Potential for NORVIR to Affect Other Drugs
7.2 Established and Other Potentially Significant Drug Interactions
8 USE IN SPECIFIC POPULATIONS
8.1 Pregnancy
8.2 Lactation
8.3 Females and Males of Reproductive Potential
8.4 Pediatric Use
8.5 Geriatric Use
8.6 Hepatic Impairment
10 OVERDOSAGE
10.1 Acute Overdosage - Human Overdose Experience
10.2 Management of Overdosage
11 DESCRIPTION
12 CLINICAL PHARMACOLOGY
12.1 Mechanism of Action
12.3 Pharmacokinetics
12.4 Microbiology
13 NONCLINICAL TOXICOLOGY
13.1 Carcinogenesis, Mutagenesis, Impairment of Fertility
14 CLINICAL STUDIES
14.1 Advanced Patients with Prior Antiretroviral Therapy
14.2 Patients without Prior Antiretroviral Therapy
15 REFERENCES
16 HOW SUPPLIED/STORAGE AND HANDLING
16.1 NORVIR Tablets, 100 mg Ritonavir
16.2 NORVIR Oral Solution, 80 mg per mL Ritonavir
17 PATIENT COUNSELING INFORMATION

*
Sections or subsections omitted from the full prescribing information are not listed.

1 INDICATIONS AND USAGE

NORVIR is indicated in combination with other antiretroviral agents for the treatment of HIV-1 infection.

2 DOSAGE AND ADMINISTRATION

NORVIR is administered orally. NORVIR tablets should be swallowed whole, and not chewed, broken or crushed. Take NORVIR with meals. Patients may improve the taste of NORVIR oral solution by mixing with chocolate milk, Ensure®, or Advera® within one hour of dosing.

General Dosing Guidelines

Patients who take the 600 mg twice daily soft gel capsule NORVIR dose may experience more gastrointestinal side effects such as nausea, vomiting, abdominal pain or diarrhea when switching from the soft gel capsule to the tablet formulation because of greater maximum plasma concentration (Cmax) achieved with the tablet formulation relative to the soft gel capsule [see Clinical Pharmacology (12.3)]. Patients should also be aware that these adverse events (gastrointestinal or paresthesias) may diminish as therapy is continued.

Dose Modification for NORVIR

Dose reduction of NORVIR is necessary when used with other protease inhibitors: atazanavir, darunavir, fosamprenavir, saquinavir, and tipranavir.

Prescribers should consult the full prescribing information and clinical study information of these protease inhibitors if they are co-administered with a reduced dose of ritonavir [see Warnings and Precautions (5.1), and Drug Interactions (7)].

2.1 Adult Patients

Recommended Dosage for Treatment of HIV-1:

The recommended dosage of ritonavir is 600 mg twice daily by mouth to be taken with meals. Use of a dose titration schedule may help to reduce treatment-emergent adverse events while maintaining appropriate ritonavir plasma levels. Ritonavir should be started at no less than 300 mg twice daily and increased at 2 to 3 day intervals by 100 mg twice daily. The maximum dose of 600 mg twice daily should not be exceeded upon completion of the titration.

Pregnant Women

NORVIR oral solution is not recommended during pregnancy due to its alcohol content. NORVIR oral solution contains the excipients alcohol (43.2% v/v) and propylene glycol (26.57% w/v) [see Use in Specific Populations (8.1)].

2.2 Pediatric Patients

Ritonavir should be used in combination with other antiretroviral agents [see Dosage and Administration (2)]. The recommended dosage of ritonavir in children greater than 1 month is 350 to 400 mg per m2 twice daily by mouth to be taken with meals and should not exceed 600 mg twice daily. Ritonavir should be started at 250 mg per m2 twice daily and increased at 2 to 3 day intervals by 50 mg per m2 twice daily. If patients do not tolerate 400 mg per m2 twice daily due to adverse events, the highest tolerated dose may be used for maintenance therapy in combination with other antiretroviral agents, however, alternative therapy should be considered. When possible, dose should be administered using a calibrated dosing syringe.

NORVIR oral solution should not be administered to neonates before a postmenstrual age (first day of the mother’s last menstrual period to birth plus the time elapsed after birth) of 44 weeks has been attained [see Warnings and Precautions (5.2)].

NORVIR oral solution contains 43.2% (v/v) alcohol and 26.57% (w/v) propylene glycol. Special attention should be given to accurate calculation of the dose of NORVIR, transcription of the medication order, dispensing information and dosing instructions to minimize the risk for medication errors, and overdose. This is especially important for young children. Total amounts of alcohol and propylene glycol from all medicines that are to be given to pediatric patients 1 to 6 months of age should be taken into account in order to avoid toxicity from these excipients [see Warnings and Precautions (5.2) and Overdosage (10)].

Table 1. Pediatric Dosage Guidelines
Body Surface Area (m2) Twice Daily Dose
250 mg per m2 Twice Daily Dose
300 mg per m2 Twice Daily Dose
350 mg per m2 Twice Daily Dose
400 mg per m2
0.20 0.6 mL (50 mg) 0.75 mL (60 mg) 0.9 mL (70 mg) 1.0 mL (80 mg)
0.25 0.8 mL (62.5 mg) 0.9 mL (75 mg) 1.1 mL (87.5 mg) 1.25 mL (100 mg)
0.50 1.6 mL (125 mg) 1.9 mL (150 mg) 2.2 mL (175 mg) 2.5 mL (200 mg)
0.75 2.3 mL (187.5 mg) 2.8 mL (225 mg) 3.3 mL (262.5 mg) 3.75 mL (300 mg)
1.00 3.1 mL (250 mg) 3.75 mL (300 mg) 4.4 mL (350 mg) 5 mL (400 mg)
1.25 3.9 mL (312.5 mg) 4.7 mL (375 mg) 5.5 mL (437.5 mg) 6.25 mL (500 mg)
1.50 4.7 mL (375 mg) 5.6 mL (450 mg) 6.6 mL (525 mg) 7.5 mL (600 mg)

Body surface area (BSA) can be calculated as follows1:

[norvir equation]

3 DOSAGE FORMS AND STRENGTHS

NORVIR Tablets

White film-coated ovaloid tablets debossed with the "a" logo and the code NK providing 100 mg ritonavir.

NORVIR Oral Solution

Orange-colored liquid containing 600 mg ritonavir per 7.5 mL marked dosage cup (80 mg per mL).

4 CONTRAINDICATIONS

When co-administering NORVIR with other protease inhibitors, see the full prescribing information for that protease inhibitor including contraindication information.
NORVIR is contraindicated in patients with known hypersensitivity (e.g., toxic epidermal necrolysis (TEN) or Stevens-Johnson syndrome) to ritonavir or any of its ingredients.
NORVIR is contraindicated with drugs that are highly dependent on CYP3A for clearance and for which elevated plasma concentrations are associated with serious and/or life-threatening reactions.
NORVIR is contraindicated with drugs that are potent CYP3A inducers where significantly reduced lopinavir plasma concentrations may be associated with the potential for loss of virologic response and possible resistance and cross-resistance.

Table 2. Drugs that are Contraindicated with NORVIR
Drug Class Drugs Within Class That Are Contraindicated With NORVIR** Clinical Comments
Alpha1-adrenoreceptor antagonist Alfuzosin HCL Potential for hypotension.
Antiarrhythmic Amiodarone, dronedarone, flecainide, propafenone, quinidine Potential for cardiac arrhythmias.
Antifungal Voriconazole Voriconazole is contraindicated with ritonavir doses of 400 mg every 12 hours or greater due to the potential for loss of antifungal response.
Anti-gout Colchicinea Potential for serious and/or life-threatening reactions in patients with renal and/or hepatic impairment.
Antipsychotics Lurasidone
Pimozide Potential for serious and/or life-threatening reactions.
Potential for serious and/or life‑threatening reactions such as cardiac arrhythmias.
Ergot Derivatives Dihydroergotamine, ergotamine, methylergonovine Potential for acute ergot toxicity characterized by vasospasm and ischemia of the extremities and other tissues including the central nervous system.
GI Motility Agent Cisapride Potential for cardiac arrhythmias.
Herbal Products St. John's Wort (hypericum perforatum) May lead to loss of virologic response and possible resistance to NORVIR or to the class of protease inhibitors.
HMG-CoA Reductase Inhibitors Lovastatin, simvastatin Potential for myopathy including rhabdomyolysis.
PDE5 inhibitor Sildenafilb (Revatio®) when used for the treatment of pulmonary arterial hypertension (PAH) Potential for sildenafil-associated adverse events, including visual abnormalities, hypotension, prolonged erection, and syncope.
Sedative/hypnotics Oral midazolamc, triazolam Prolonged or increased sedation or respiratory depression.
a see Drug Interactions (7), TABLE 5 for colchicine doses in patients with normal hepatic and renal function.
b see Drug Interactions (7), TABLE 5 for co-administration of sildenafil in patients with erectile dysfunction.
c see Drug Interactions (7), TABLE 5 for parenterally administered midazolam.

5 WARNINGS AND PRECAUTIONS

5.1 Risk of Serious Adverse Reactions Due to Drug Interactions

Initiation of NORVIR, a CYP3A inhibitor, in patients receiving medications metabolized by CYP3A or initiation of medications metabolized by CYP3A in patients already receiving NORVIR, may increase plasma concentrations of medications metabolized by CYP3A. Initiation of medications that inhibit or induce CYP3A may increase or decrease concentrations of NORVIR, respectively. These interactions may lead to:

Clinically significant adverse reactions, potentially leading to severe, life-threatening, or fatal events from greater exposures of concomitant medications.
Clinically significant adverse reactions from greater exposures of NORVIR.
Loss of therapeutic effect of NORVIR and possible development of resistance.

When co-administering NORVIR with other protease inhibitors, see the full prescribing information for that protease inhibitor including important Warnings and Precautions.

See Table 5 for steps to prevent or manage these possible and known significant drug interactions, including dosing recommendations [see Drug Interactions (7)]. Consider the potential for drug interactions prior to and during NORVIR therapy; review concomitant medications during NORVIR therapy, and monitor for the adverse reactions associated with the concomitant medications [see Contraindications(4) and Drug Interactions (7)].

5.2 Toxicity in Preterm Neonates

NORVIR oral solution contains the excipients alcohol (43.2% v/v) and propylene glycol (26.57% w/v). When administered concomitantly with propylene glycol, ethanol competitively inhibits the metabolism of propylene glycol, which may lead to elevated concentrations. Preterm neonates may be at an increased risk of propylene glycol-associated adverse events due to diminished ability to metabolize propylene glycol, thereby leading to accumulation and potential adverse events. Postmarketing life-threatening cases of cardiac toxicity (including complete AV block, bradycardia, and cardiomyopathy), lactic acidosis, acute renal failure, CNS depression and respiratory complications leading to death have been reported, predominantly in preterm neonates receiving lopinavir/ritonavir oral solution which also contains the excipients alcohol and propylene glycol.

NORVIR oral solution should not be used in preterm neonates in the immediate postnatal period because of possible toxicities. However, if the benefit of using NORVIR oral solution to treat HIV infection in infants immediately after birth outweighs the potential risks, infants should be monitored closely for increases in serum osmolality and serum creatinine, and for toxicity related to NORVIR oral solution including: hyperosmolality, with or without lactic acidosis, renal toxicity, CNS depression (including stupor, coma, and apnea), seizures, hypotonia, cardiac arrhythmias and ECG changes, and hemolysis. Total amounts of alcohol and propylene glycol from all medicines that are to be given to infants should be taken into account in order to avoid toxicity from these excipients [see Dosage and Administration (2.2) and Overdosage (10)].

5.3 Hepatic Reactions

Hepatic transaminase elevations exceeding 5 times the upper limit of normal, clinical hepatitis, and jaundice have occurred in patients receiving NORVIR alone or in combination with other antiretroviral drugs (see Table 4). There may be an increased risk for transaminase elevations in patients with underlying hepatitis B or C. Therefore, caution should be exercised when administering NORVIR to patients with pre-existing liver diseases, liver enzyme abnormalities, or hepatitis. Increased AST/ALT monitoring should be considered in these patients, especially during the first three months of NORVIR treatment [see Use in Specific Populations (8.6)].

There have been postmarketing reports of hepatic dysfunction, including some fatalities. These have generally occurred in patients taking multiple concomitant medications and/or with advanced AIDS.

5.4 Pancreatitis

Pancreatitis has been observed in patients receiving NORVIR therapy, including those who developed hypertriglyceridemia. In some cases fatalities have been observed. Patients with advanced HIV disease may be at increased risk of elevated triglycerides and pancreatitis [see Warnings and Precautions (5.7)]. Pancreatitis should be considered if clinical symptoms (nausea, vomiting, abdominal pain) or abnormalities in laboratory values (such as increased serum lipase or amylase values) suggestive of pancreatitis should occur. Patients who exhibit these signs or symptoms should be evaluated and NORVIR therapy should be discontinued if a diagnosis of pancreatitis is made.

5.5 Allergic Reactions/Hypersensitivity

Allergic reactions including urticaria, mild skin eruptions, bronchospasm, and angioedema have been reported. Cases of anaphylaxis, toxic epidermal necrolysis (TEN), and Stevens-Johnson syndrome have also been reported. Discontinue treatment if severe reactions develop.

5.6 PR Interval Prolongation

Ritonavir prolongs the PR interval in some patients. Post marketing cases of second or third degree atrioventricular block have been reported in patients.

NORVIR should be used with caution in patients with underlying structural heart disease, preexisting conduction system abnormalities, ischemic heart disease, cardiomyopathies, as these patients may be at increased risk for developing cardiac conduction abnormalities.

The impact on the PR interval of co-administration of ritonavir with other drugs that prolong the PR interval (including calcium channel blockers, beta-adrenergic blockers, digoxin and atazanavir) has not been evaluated. As a result, co-administration of ritonavir with these drugs should be undertaken with caution, particularly with those drugs metabolized by CYP3A. Clinical monitoring is recommended [see Drug Interactions (7), and Clinical Pharmacology (12.3)].

5.7 Lipid Disorders

Treatment with NORVIR therapy alone or in combination with saquinavir has resulted in substantial increases in the concentration of total cholesterol and triglycerides [see Adverse Reactions (6.1)]. Triglyceride and cholesterol testing should be performed prior to initiating NORVIR therapy and at periodic intervals during therapy. Lipid disorders should be managed as clinically appropriate, taking into account any potential drug-drug interactions with NORVIR and HMG CoA reductase inhibitors [see Contraindications (4)and Drug Interactions (7)].

5.8 Diabetes Mellitus/Hyperglycemia

New onset diabetes mellitus, exacerbation of pre-existing diabetes mellitus, and hyperglycemia have been reported during postmarketing surveillance in HIV-infected patients receiving protease inhibitor therapy. Some patients required either initiation or dose adjustments of insulin or oral hypoglycemic agents for treatment of these events. In some cases, diabetic ketoacidosis has occurred. In those patients who discontinued protease inhibitor therapy, hyperglycemia persisted in some cases. Because these events have been reported voluntarily during clinical practice, estimates of frequency cannot be made and a causal relationship between protease inhibitor therapy and these events has not been established.Consider monitoring for hyperglycemia, new onset diabetes mellitus, or an exacerbation of diabetes mellitus in patients treated with NORVIR.

5.9 Immune Reconstitution Syndrome

Immune reconstitution syndrome has been reported in HIV-infected patients treated with combination antiretroviral therapy, including NORVIR. During the initial phase of combination antiretroviral treatment, patients whose immune system responds may develop an inflammatory response to indolent or residual opportunistic infections (such as Mycobacterium avium infection, cytomegalovirus, Pneumocystis jiroveci pneumonia, or tuberculosis), which may necessitate further evaluation and treatment.

Autoimmune disorders (such as Graves’ disease, polymyositis, and Guillain-Barré syndrome) have also been reported to occur in the setting of immune reconstitution, however, the time to onset is more variable, and can occur many months after initiation of treatment.

5.10 Fat Redistribution

Redistribution/accumulation of body fat including central obesity, dorsocervical fat enlargement (buffalo hump), peripheral wasting, facial wasting, breast enlargement, and "cushingoid appearance" have been observed in patients receiving antiretroviral therapy. The mechanism and long-term consequences of these events are currently unknown. A causal relationship has not been established.

5.11 Patients with Hemophilia

There have been reports of increased bleeding, including spontaneous skin hematomas and hemarthrosis, in patients with hemophilia type A and B treated with protease inhibitors. In some patients additional factor VIII was given. In more than half of the reported cases, treatment with protease inhibitors was continued or reintroduced. A causal relationship between protease inhibitor therapy and these events has not been established.

5.12 Resistance/Cross-resistance

Varying degrees of cross-resistance among protease inhibitors have been observed. Continued administration of ritonavir 600 mg twice daily following loss of viral suppression may increase the likelihood of cross-resistance to other protease inhibitors [see Microbiology (12.4)].

5.13 Laboratory Tests

Ritonavir has been shown to increase triglycerides, cholesterol, SGOT (AST), SGPT (ALT), GGT, CPK, and uric acid. Appropriate laboratory testing should be performed prior to initiating NORVIR therapy and at periodic intervals or if any clinical signs or symptoms occur during therapy.

6 ADVERSE REACTIONS

The following adverse reactions are discussed in greater detail in other sections of the labeling.

Drug Interactions [see Warnings and Precautions (5.1)]
Hepatotoxicity [see Warnings and Precautions (5.3)]
Pancreatitis [see Warnings and Precautions (5.4)]
Allergic Reactions/Hypersensitivity [see Warnings and Precautions (5.5)]

When co-administering NORVIR with other protease inhibitors, see the full prescribing information for that protease inhibitor including adverse reactions.

6.1 Clinical Trial Experience

Because clinical trials are conducted under widely varying conditions, adverse reactions rates observed in the clinical trials of a drug cannot be directly compared to rates in the clinical trials of another drug and may not reflect the rates observed in practice.

Adverse Reactions in Adults

The safety of NORVIR alone and in combination with other antiretroviral agents was studied in 1,755 adult patients. Table 3 lists treatment-emergent Adverse Reactions (with possible or probable relationship to study drug) occurring in greater than or equal to 1% of adult patients receiving NORVIR in combined Phase II/IV studies.

The most frequently reported adverse drug reactions among patients receiving NORVIR alone or in combination with other antiretroviral drugs were gastrointestinal (including diarrhea, nausea, vomiting, abdominal pain (upper and lower)), neurological disturbances (including paresthesia and oral paresthesia), rash, and fatigue/asthenia.

Table 3. Treatment-Emergent Adverse Reactions (With Possible or Probable Relationship to Study Drug) Occurring in greater than or equal to 1% of Adult Patients Receiving NORVIR in Combined Phase II/IV Studies (N = 1,755)
Adverse Reactions n %
Eye disorders
Blurred vision 113 6.4
Gastrointestinal disorders
Abdominal Pain (upper and lower)* 464 26.4
Diarrhea including severe with electrolyte imbalance* 1,192 67.9
Dyspepsia 201 11.5
Flatulence 142 8.1
Gastrointestinal hemorrhage* 41 2.3
Gastroesophageal reflux disease (GERD) 19 1.1
Nausea 1,007 57.4
Vomiting* 559 31.9
General disorders and administration site conditions
Fatigue including asthenia* 811 46.2
Hepatobiliary disorders
Blood bilirubin increased (including jaundice)* 25 1.4
Hepatitis (including increased AST, ALT, GGT)* 153 8.7
Immune system disorders
Hypersensitivity including urticaria and face edema* 114 8.2
Metabolism and nutrition disorders
Edema and peripheral edema* 110 6.3
Gout* 24 1.4
Hypercholesterolemia* 52 3.0
Hypertriglyceridemia* 158 9.0
Lipodystrophy acquired* 51 2.9
Musculoskeletal and connective tissue disorders
Arthralgia and back pain* 326 18.6
Myopathy/creatine phosphokinase increased* 66 3.8
Myalgia 156 8.9
Nervous system disorders
Dizziness* 274 15.6
Dysgeusia* 285 16.2
Paresthesia (including oral paresthesia)* 889 50.7
Peripheral neuropathy 178 10.1
Syncope* 58 3.3
Psychiatric disorders
Confusion* 52 3.0
Disturbance in attention 44 2.5
Renal and urinary disorders
Increased urination* 74 4.2
Respiratory, thoracic and mediastinal disorders
Coughing* 380 21.7
Oropharyngeal Pain* 279 15.9
Skin and subcutaneous tissue disorders
Acne* 67 3.8
Pruritus* 214 12.2
Rash (includes erythematous and maculopapular)* 475 27.1
Vascular disorders
Flushing, feeling hot* 232 13.2
Hypertension* 58 3.3
Hypotension including orthostatic hypotension* 30 1.7
Peripheral coldness* 21 1.2
* Represents a medical concept including several similar MedDRA PTs

Laboratory Abnormalities in Adults

Table 4 shows the percentage of adult patients who developed marked laboratory abnormalities.

Table 4. Percentage of Adult Patients, by Study and Treatment Group, with Chemistry and Hematology Abnormalities Occurring in greater than 3% of Patients Receiving NORVIR
Study 245
Naive Patients Study 247
Advanced Patients Study 462 PI-Naive Patients
Variable Limit NORVIR plus ZDV NORVIR ZDV NORVIR Placebo NORVIR plus Saquinavir
Chemistry High
Cholesterol > 240 mg/dL 30.7 44.8 9.3 36.5 8.0 65.2
CPK > 1000 IU/L 9.6 12.1 11.0 9.1 6.3 9.9
GGT > 300 IU/L 1.8 5.2 1.7 19.6 11.3 9.2
SGOT (AST) > 180 IU/L 5.3 9.5 2.5 6.4 7.0 7.8
SGPT (ALT) > 215 IU/L 5.3 7.8 3.4 8.5 4.4 9.2
Triglycerides > 800 mg/dL 9.6 17.2 3.4 33.6 9.4 23.4
Triglycerides > 1500 mg/dL 1.8 2.6 - 12.6 0.4 11.3
Triglycerides Fasting > 1500 mg/dL 1.5 1.3 - 9.9 0.3 -
Uric Acid > 12 mg/dL - - - 3.8 0.2 1.4
Hematology Low
Hematocrit < 30% 2.6 - 0.8 17.3 22.0 0.7
Hemoglobin < 8.0 g/dL 0.9 - - 3.8 3.9 -
Neutrophils ≤ 0.5 x 109/L - - - 6.0 8.3 -
RBC < 3.0 x 1012/L 1.8 - 5.9 18.6 24.4 -
WBC < 2.5 x 109/L - 0.9 6.8 36.9 59.4 3.5
- Indicates no events reported.

Adverse Reactions in Pediatric Patients

NORVIR has been studied in 265 pediatric patients greater than 1 month to 21 years of age. The adverse event profile observed during pediatric clinical trials was similar to that for adult patients.

Vomiting, diarrhea, and skin rash/allergy were the only drug-related clinical adverse events of moderate to severe intensity observed in greater than or equal to 2% of pediatric patients enrolled in NORVIR clinical trials.

Laboratory Abnormalities in Pediatric Patients

The following Grade 3-4 laboratory abnormalities occurred in greater than 3% of pediatric patients who received treatment with NORVIR either alone or in combination with reverse transcriptase inhibitors: neutropenia (9%), hyperamylasemia (7%), thrombocytopenia (5%), anemia (4%), and elevated AST (3%).

6.2 Postmarketing Experience

The following adverse events (not previously mentioned in the labeling) have been reported during post-marketing use of NORVIR. Because these reactions are reported voluntarily from a population of unknown size, it is not possible to reliably estimate their frequency or establish a causal relationship to NORVIR exposure.

Body as a Whole

Dehydration, usually associated with gastrointestinal symptoms, and sometimes resulting in hypotension, syncope, or renal insufficiency has been reported. Syncope, orthostatic hypotension, and renal insufficiency have also been reported without known dehydration.

Co-administration of ritonavir with ergotamine or dihydroergotamine has been associated with acute ergot toxicity characterized by vasospasm and ischemia of the extremities and other tissues including the central nervous system.

Cardiovascular System

First-degree AV block, second-degree AV block, third-degree AV block, right bundle branch block have been reported [see Warnings and Precautions (5.6)].

Cardiac and neurologic events have been reported when ritonavir has been co-administered with disopyramide, mexiletine, nefazodone, fluoxetine, and beta blockers. The possibility of drug interaction cannot be excluded.

Endocrine System

Cushing's syndrome and adrenal suppression have been reported when ritonavir has been co-administered with fluticasone propionate or budesonide.

Nervous System

There have been postmarketing reports of seizure. Also, see Cardiovascular System.

Skin and subcutaneous tissue disorders

Toxic epidermal necrolysis (TEN) has been reported.

7 DRUG INTERACTIONS

See also Contraindications (4), Warnings and Precautions (5.1), and Clinical Pharmacology (12.3)

When co-administering NORVIR with other protease inhibitors (atazanavir, darunavir, fosamprenavir, saquinavir, and tipranavir), see the full prescribing information for that protease inhibitor including important information for drug interactions.

7.1 Potential for NORVIR to Affect Other Drugs

Ritonavir is an inhibitor of cytochrome P450 3A (CYP3A) and may increase plasma concentrations of agents that are primarily metabolized by CYP3A. Agents that are extensively metabolized by CYP3A and have high first pass metabolism appear to be the most susceptible to large increases in AUC (greater than 3-fold) when co-administered with ritonavir. Thus, co-administration of NORVIR with drugs highly dependent on CYP3A for clearance and for which elevated plasma concentrations are associated with serious and/or life-threatening events is contraindicated. Co-administration with other CYP3A substrates may require a dose adjustment or additional monitoring as shown in Table 5.

Ritonavir also inhibits CYP2D6 to a lesser extent. Co-administration of substrates of CYP2D6 with ritonavir could result in increases (up to 2-fold) in the AUC of the other agent, possibly requiring a proportional dosage reduction. Ritonavir also appears to induce CYP3A, CYP1A2, CYP2C9, CYP2C19, and CYP2B6 as well as other enzymes, including glucuronosyl transferase.

7.2 Established and Other Potentially Significant Drug Interactions

Table 5 provides a list of established or potentially clinically significant drug interactions. Alteration in dose or regimen may be recommended based on drug interaction studies or predicted interaction [see Clinical Pharmacology (12.3)] for magnitude of interaction.

Table 5. Established and Other Potentially Significant Drug Interactions
Concomitant Drug Class:
Drug Name Effect on Concentration of Ritonavir or Concomitant Drug Clinical Comment
HIV-Antiviral Agents
HIV-1 Protease Inhibitor:
atazanavir
darunavir
fosamprenavir ↑ amprenavir
↑ atazanavir
↑ darunavir See the complete prescribing information for fosamprenavir, atazanavir, darunavir for details on co-administration with ritonavir.
HIV-1 Protease Inhibitor:
indinavir ↑ indinavir Appropriate doses for this combination, with respect to efficacy and safety, have not been established.
HIV-1 Protease Inhibitor:
saquinavir ↑ saquinavir See the complete prescribing information for saquinavir for details on co-administration of saquinavir and ritonavir.
Saquinavir/ritonavir in combination with rifampin is not recommended due to the risk of severe hepatotoxicity (presenting as increased hepatic transaminases) if the three drugs are given together.
HIV-1 Protease Inhibitor:
tipranavir ↑ tipranavir See the complete prescribing information for tipranavir for details on co-administration of tipranavir and ritonavir.
Non-Nucleoside Reverse Transcriptase Inhibitor:
delavirdine ↑ ritonavir Appropriate doses of this combination with respect to safety and efficacy have not been established.
HIV-1 CCR5 – antagonist: maraviroc ↑ maraviroc See the complete prescribing information for maraviroc for details on co-administration of maraviroc and ritonavir-containing protease inhibitors.
Integrase Inhibitor:
raltegravir ↓ raltegravir The effects of ritonavir on raltegravir with ritonavir dosage regimens greater than 100 mg twice daily have not been evaluated, however raltegravir concentrations may be decreased with ritonavir coadministration.
Other Agents
Analgesics, Narcotic:
tramadol,
propoxyphene,
methadone,
fentanyl ↑ analgesics
↓ methadone
↑ fentanyl A dose decrease may be needed for these drugs when co-administered with ritonavir.
Dosage increase of methadone may be considered.
Careful monitoring of therapeutic and adverse effects (including potentially fatal respiratory depression) is recommended when fentanyl is concomitantly administered with NORVIR.
Anesthetic:
meperidine ↓ meperidine/ ↑ normeperidine (metabolite) Dosage increase and long-term use of meperidine with ritonavir are not recommended due to the increased concentrations of the metabolite normeperidine which has both analgesic activity and CNS stimulant activity (e.g., seizures).
Antialcoholics:
disulfiram/ metronidazole Ritonavir formulations contain alcohol, which can produce disulfiram-like reactions when co-administered with disulfiram or other drugs that produce this reaction (e.g., metronidazole).
Antiarrhythmics:
disopyramide, lidocaine, mexiletine ↑ antiarrhythmics For contraindicated antiarrhythmics [see Contraindications (4)].
Caution is warranted and therapeutic concentration monitoring is recommended for antiarrhythmics when co-administered with ritonavir, if available.
Anticancer Agents:
dasatinib, nilotinib,
vincristine, vinblastine ↑ anticancer agents For vincristine and vinblastine, consideration should be given to temporarily withholding the ritonavir containing antiretroviral regimen in patients who develop significant hematologic or gastrointestinal side effects when ritonavir is administered concurrently with vincristine or vinblastine. Clinicians should be aware that if the ritonavir containing regimen is withheld for a prolonged period, consideration should be given to altering the regimen to not include a CYP3A or P-gp inhibitor in order to control HIV-1 viral load.
A decrease in the dosage or an adjustment of the dosing interval of nilotinib and dasatinib may be necessary for patients requiring co-administration with strong CYP3A inhibitors such as NORVIR. Please refer to the nilotinib and dasatinib prescribing information for dosing instructions.
Anticoagulant:
warfarin ↑↓ warfarin Initial frequent monitoring of the INR during ritonavir and warfarin co-administration is recommended.
Anticoagulant:
rivaroxaban ↑ rivaroxaban Avoid concomitant use of rivaroxaban and ritonavir. Co-administration of ritonavir and rivaroxaban may lead to risk of increased bleeding.
Anticonvulsants:
carbamazepine, clonazepam, ethosuximide ↑ anticonvulsants A dose decrease may be needed for these drugs when co-administered with ritonavir and therapeutic concentration monitoring is recommended for these anticonvulsants, if available.
Anticonvulsants:
divalproex, lamotrigine, phenytoin ↓ anticonvulsants A dose increase may be needed for these drugs when co-administered with ritonavir and therapeutic concentration monitoring is recommended for these anticonvulsants, if available.
Antidepressants:
nefazodone,
selective serotonin
reuptake inhibitors
(SSRIs): e.g.
fluoxetine,
paroxetine,
tricyclics: e.g.
amitriptyline,
nortriptyline ↑ antidepressants A dose decrease may be needed for these drugs when co-administered with ritonavir.
Antidepressant:
bupropion ↓ bupropion
↓ active metabolite, hydroxybupropion Patients receiving ritonavir and bupropion concurrently should be monitored for an adequate clinical response to bupropion.
Antidepressant:
desipramine ↑ desipramine Dosage reduction and concentration monitoring of desipramine is recommended.
Antidepressant:
trazodone ↑ trazodone Adverse events of nausea, dizziness, hypotension and syncope have been observed following co-administration of trazodone and NORVIR. A lower dose of trazodone should be considered.
Antiemetic:
dronabinol ↑ dronabinol A dose decrease of dronabinol may be needed when co-administered with ritonavir.
Antifungals:
ketoconazole
itraconazole
voriconazole ↑ ketoconazole
↑ itraconazole
↓ voriconazole

For contraindicated antifungals, [see Contraindications (4)].

High doses of ketoconazole or itraconazole (greater than 200 mg per day) are not recommended.
Co-administration of voriconazole and ritonavir doses of 400 mg every 12 hours or greater is contraindicated [see Contraindications (4)]. Co-administration of voriconazole and ritonavir 100 mg should be avoided, unless an assessment of the benefit/risk to the patient justifies the use of voriconazole.

Anti-gout:
colchicine ↑ colchicine

Concomitant administration with colchicine is contraindicated in patients with renal and/or hepatic impairment [see Contraindications (4)].

For patients with normal renal or hepatic function:

Treatment of gout flares-co-administration of colchicine in patients on ritonavir:

0.6 mg (one tablet) for one dose, followed by 0.3 mg (half tablet) one hour later. Dose to be repeated no earlier than three days.

Prophylaxis of gout flares-co-administration of colchicine in patients on ritonavir:

If the original colchicine regimen was 0.6 mg twice a day, the regimen should be adjusted to 0.3 mg once a day.

If the original colchicine regimen was 0.6 mg once a day, the regimen should be adjusted to 0.3 mg once every other day.

Treatment of familial Mediterranean fever (FMF)-co-administration of colchicine in patients on ritonavir:

Maximum daily dose of 0.6 mg (may be given as 0.3 mg twice a day).
Anti-infective:
clarithromycin ↑ clarithromycin For patients with renal impairment, adjust clarithromycin dose as follows:

For patients with CLCR 30 to 60 mL per min the dose of clarithromycin should be reduced by 50%.
For patients with CLCR less than 30 mL per min the dose of clarithromycin should be decreased by 75%.

No dose adjustment for patients with normal renal function is necessary.
Antimycobacterial:
bedaquiline ↑ bedaquiline Bedaquiline should only be used with ritonavir if the benefit of co-administration outweighs the risk.
Antimycobacterial:
rifabutin ↑ rifabutin and rifabutin metabolite Dosage reduction of rifabutin by at least three-quarters of the usual dose of 300 mg per day is recommended (e.g., 150 mg every other day or three times a week). Further dosage reduction may be necessary.
Antimycobacterial:
rifampin ↓ ritonavir May lead to loss of virologic response. Alternate antimycobacterial agents such as rifabutin should be considered.
Antiparasitic:
atovaquone ↓ atovaquone Clinical significance is unknown; however, increase in atovaquone dose may be needed.
Antiparasitic:
quinine ↑ quinine A dose decrease of quinine may be needed when co-administered with ritonavir.
Antipsychotics:
perphenazine,
risperidone,
thioridazine ↑ antipsychotics For contraindicated antipsychotics, [see Contraindications (4)].
A dose decrease may be needed for these drugs when co-administered with ritonavir.
Antipsychotics:
quetiapine ↑ quetiapine

Initiation of NORVIR in patients taking quetiapine:

Consider alternative antiretroviral therapy to avoid increases in quetiapine exposures. If coadministration is necessary, reduce the quetiapine dose to 1/6 of the current dose and monitor for quetiapine-associated adverse reactions. Refer to the quetiapine prescribing information for recommendations on adverse reaction monitoring.

Initiation of quetiapine in patients taking NORVIR:

Refer to the quetiapine prescribing information for initial dosing and titration of quetiapine.
β-Blockers:
metoprolol, timolol ↑ beta-blockers Caution is warranted and clinical monitoring of patients is recommended. A dose decrease may be needed for these drugs when co-administered with ritonavir.
Bronchodilator:
theophylline ↓ theophylline Increased dosage of theophylline may be required; therapeutic monitoring should be considered.
Calcium channel blockers:
diltiazem, nifedipine, verapamil ↑ calcium channel blockers Caution is warranted and clinical monitoring of patients is recommended. A dose decrease may be needed for these drugs when co-administered with ritonavir.
Digoxin ↑ digoxin Concomitant administration of ritonavir with digoxin may increase digoxin levels. Caution should be exercised when co-administering ritonavir with digoxin, with appropriate monitoring of serum digoxin levels.
Endothelin receptor antagonists: bosentan ↑ bosentan

Co-administration of bosentan in patients on ritonavir:

In patients who have been receiving ritonavir for at least 10 days, start bosentan at 62.5 mg once daily or every other day based upon individual tolerability.

Co-administration of ritonavir in patients on bosentan:

Discontinue use of bosentan at least 36 hours prior to initiation of ritonavir.

After at least 10 days following the initiation of ritonavir, resume bosentan at 62.5 mg once daily or every other day based upon individual tolerability.
Hepatitis C direct acting antiviral:
simeprevir ↑simeprevir It is not recommended to co-administer ritonavir with simeprevir.
HMG-CoA Reductase Inhibitor:
atorvastatin
rosuvastatin ↑ atorvastatin
↑ rosuvastatin For contraindicated HMG-CoA reductase inhibitors, [see Contraindications (4)].
Titrate atorvastatin and rosuvastatin dose carefully and use the lowest necessary dose.
If NORVIR is used with another protease inhibitor, see the complete prescribing information for the concomitant protease inhibitor for details on co-administration with atorvastatin and rosuvastatin.
Immunosuppressants:
cyclosporine, tacrolimus, sirolimus (rapamycin) ↑ immunosuppressants Therapeutic concentration monitoring is recommended for immunosuppressant agents when co-administered with ritonavir.
Inhaled or Intranasal
Steroid: e.g.
fluticasone
budesonide ↑ glucocorticoids

Concomitant use of ritonavir and fluticasone or other glucocorticoids that are metabolized by CYP3A is not recommended unless the potential benefit of treatment outweighs the risk of systemic corticosteroid effects. Concomitant use may result in increased steroid concentrations and reduced serum cortisol concentrations.

Systemic corticosteroid effects including Cushing's syndrome and adrenal suppression have been reported during postmarketing use in patients when ritonavir has been coadministered with fluticasone propionate or budesonide.

Long-acting beta-adrenoceptor agonist: salmeterol ↑ salmeterol Concurrent administration of salmeterol and ritonavir is not recommended. The combination may result in increased risk of cardiovascular adverse events associated with salmeterol, including QT prolongation, palpitations and sinus tachycardia.
Oral Contraceptives or Patch Contraceptives:
ethinyl estradiol ↓ ethinyl estradiol Alternate methods of contraception should be considered.
PDE5 Inhibitors:
avanafil
sildenafil,
tadalafil,
vardenafil ↑ avanafil
↑ sildenafil
↑ tadalafil
↑ vardenafil For contraindicated PDE5 inhibitors, [see Contraindications (4)].
Do not use ritonavir with avanafil because a safe and effective avanafil dosage regimen has not been established.
Particular caution should be used when prescribing sildenafil, tadalafil or vardenafil in patients receiving ritonavir. Coadministration of ritonavir with these drugs may result in an increase in PDE5 inhibitor associated adverse events, including hypotension, syncope, visual changes, and prolonged erection.
Use of PDE5 inhibitors for pulmonary arterial hypertension (PAH):
Sildenafil (Revatio®) is contraindicated [see Contraindications (4)].
The following dose adjustments are recommended for use of tadalafil (AdcircaTM) with ritonavir:

Co-administration of ADCIRCA in patients on ritonavir:

In patients receiving ritonavir for at least one week, start ADCIRCA at 20 mg once daily. Increase to 40 mg once daily based upon individual tolerability.

Co-administration of ritonavir in patients on ADCIRCA:

Avoid use of ADCIRCA during the initiation of ritonavir. Stop ADCIRCA at least 24 hours prior to starting ritonavir. After at least one week following the initiation of ritonavir, resume ADCIRCA at 20 mg once daily. Increase to 40 mg once daily based upon individual tolerability.

Use of PDE5 inhibitors for the treatment of erectile dysfunction:

It is recommended not to exceed the following doses:

Sildenafil: 25 mg every 48 hours
Tadalafil: 10 mg every 72 hours
Vardenafil: 2.5 mg every 72 hours

Use with increased monitoring for adverse events.
Sedative/hypnotics:
buspirone, clorazepate, diazepam, estazolam, flurazepam, zolpidem ↑ sedative/hypnotics A dose decrease may be needed for these drugs when co-administered with ritonavir.
Sedative/hypnotics: Parenteral midazolam
↑ midazolam For contraindicated sedative/hypnotics, [see Contraindications (4)].
Co-administration should be done in a setting which ensures close clinical monitoring and appropriate medical management in case of respiratory depression and/or prolonged sedation. Dosage reduction for midazolam should be considered, especially if more than a single dose of midazolam is administered.
Steroids (systemic): e.g.
budesonide, dexamethasone, prednisone ↑ glucocorticoids Concomitant use of glucocorticoids that are metabolized by CYP3A is not recommended unless the potential benefit of treatment outweighs the risk of systemic corticosteroid effects. This may increase the risk for development of systemic corticosteroid effects including Cushing’s syndrome and adrenal suppression.
Stimulant:
methamphetamine ↑ methamphetamine Use with caution. A dose decrease of methamphetamine may be needed when co-administered with ritonavir.

8 USE IN SPECIFIC POPULATIONS

When co-administering NORVIR with other protease inhibitors, see the full prescribing information for the co-administered protease inhibitor including important information for use in special populations.

8.1 Pregnancy

Pregnancy Exposure Registry

There is a pregnancy exposure registry that monitors pregnancy outcomes in women exposed to NORVIR during pregnancy. Healthcare providers are encouraged to register patients by calling the Antiretroviral Pregnancy Registry (APR) at 1–800–258–4263.

Risk Summary

Prospective pregnancy data from the Antiretroviral Pregnancy Registry (APR) are not sufficient to adequately assess the risk of birth defects or miscarriage. Available data from the APR show no difference in the rate of overall birth defects for ritonavir compared to the background rate for major birth defects of 2.7% in the U.S. reference population of the Metropolitan Atlanta Congenital Defects Program (MACDP) [see Data ].

In animal reproduction studies, no evidence of adverse developmental outcomes was observed with oral administration of ritonavir to pregnant rats and rabbits. During organogenesis in the rat and rabbit, systemic exposure (AUC) was approximately 1/3 lower than human exposure at the recommended daily dose. In the rat pre- and post-natal developmental study, maternal systemic exposure to ritonavir was approximately 1/2 of the exposure in humans at the recommended daily dose, based on a body surface area conversion factor [see Data].

NORVIR oral solution is not recommended during pregnancy because there is no known safe level of alcohol exposure during pregnancy [see Clinical Considerations, Dosage and Administration (2.1) and Warnings and Precautions (5.2)].

The background risk of major birth defects and miscarriage for the indicated population is unknown. All pregnancies have a background risk of birth defect, loss, or other adverse outcomes. In the U.S. general population, the estimated background risk of major birth defects and miscarriage in clinically recognized pregnancies is 2-4% and 15-20%, respectively.

Clinical Considerations

Dose Adjustments During Pregnancy and the Postpartum Period

NORVIR oral solution contains 43.2% alcohol and 26.57% propylene glycol and is not recommended during pregnancy because there is no known safe level of alcohol exposure during pregnancy [see Dosage and Administration (2.1) and Warnings and Precautions (5.2)].

Data

Human Data

Based on prospective reports to the APR of approximately 6100 live births following exposure to ritonavir-containing regimens (including over 2800 live births exposed in the first trimester and over 3200 live births exposed in the second and third trimesters), there was no difference in the rate of overall birth defects for ritonavir compared with the background birth defect rate of 2.7% in the U.S. reference population of the MACDP. The prevalence of birth defects in live births was 2.3% (95% CI: 1.7%-2.9%) following first-trimester exposure to ritonavir-containing regimens and 2.9% (95% CI: 2.3%-3.5%) following second and third trimester exposure to ritonavir-containing regimens.

While placental transfer of ritonavir and fetal ritonavir concentrations are generally low, detectable levels have been observed in cord blood samples and neonate hair.

Animal Data

Ritonavir was administered orally to pregnant rats (at 0, 15, 35, and 75 mg/kg/day) and rabbits (at 0, 25, 50, and 110 mg/kg/day) during organogenesis (on gestation days 6 through 17 and 6 through 19, respectively). No evidence of teratogenicity due to ritonavir was observed in rats and rabbits at doses producing systemic exposures (AUC) equivalent to approximately 1/3 lower than human exposure at the recommended daily dose. Developmental toxicity observed in rats (early resorptions, decreased fetal body weight and ossification delays and developmental variations) occurred at a maternally toxic dose, at an exposure equivalent to approximately 1/3 lower than human exposure at the recommended daily dose. A slight increase in the incidence of cryptorchidism was also noted in rats (at a maternally toxic dose) at an exposure approximately 1/5 lower than human exposure at the recommended daily dose. Developmental toxicity was observed in rabbits (resorptions, decreased litter size and decreased fetal weights) at maternally toxic doses approximately 1.8 times higher than the recommended daily dose, based on a body surface area conversion factor. In pre-and postnatal development study in rats, ritonavir was administered at doses of 0, 15, 35, and 60 mg/kg/day from gestation day 6 through postnatal day 20. At doses of 60 mg/kg/day, no developmental toxicity was noted with ritonavir dosage equivalent to 1/2 of the recommended daily dose, based on a body surface area conversion factor.

8.2 Lactation

Risk Summary

The Centers for Disease Control and Prevention recommend that HIV-infected mothers not breastfeed their infants to avoid risking postnatal transmission of HIV.

Limited published data reports that ritonavir is present in human milk.

There is no information on the effects of ritonavir on the breastfed infant or the effects of the drug on milk production. Because of the potential for (1) HIV transmission (in HIV-negative infants), (2) developing viral resistance (in HIV-positive infants) and (3) serious adverse reactions in a breastfed infant, instruct mothers not to breastfeed if they are receiving NORVIR.

8.3 Females and Males of Reproductive Potential

Contraception

Use of NORVIR may reduce the efficacy of combined hormonal contraceptives. Advise patients using combined hormonal contraceptives to use an effective alternative contraceptive method or an additional barrier method of contraception [see Drug Interactions (7.3)].

8.4 Pediatric Use

In HIV-infected patients age greater than 1 month to 21 years, the antiviral activity and adverse event profile seen during clinical trials and through postmarketing experience were similar to that for adult patients.

8.5 Geriatric Use

Clinical studies of NORVIR did not include sufficient numbers of subjects aged 65 and over to determine whether they respond differently from younger subjects. In general, dose selection for an elderly patient should be cautious, usually starting at the low end of the dosing range, reflecting the greater frequency of decreased hepatic, renal or cardiac function, and of concomitant disease or other drug therapy.

8.6 Hepatic Impairment

No dose adjustment of ritonavir is necessary for patients with either mild (Child-Pugh Class A) or moderate (Child-Pugh Class B) hepatic impairment. No pharmacokinetic or safety data are available regarding the use of ritonavir in subjects with severe hepatic impairment (Child-Pugh Class C), therefore, ritonavir is not recommended for use in patients with severe hepatic impairment [see Warnings and Precautions (5.3), Clinical Pharmacology (12.3)].

10 OVERDOSAGE

10.1 Acute Overdosage - Human Overdose Experience

Human experience of acute overdose with NORVIR is limited. One patient in clinical trials took NORVIR 1500 mg per day for two days. The patient reported paresthesias which resolved after the dose was decreased. A post-marketing case of renal failure with eosinophilia has been reported with ritonavir overdose.

The approximate lethal dose was found to be greater than 20 times the related human dose in rats and 10 times the related human dose in mice.

10.2 Management of Overdosage

NORVIR oral solution contains 43.2% (v/v) alcohol and 26.57% (w/v) propylene glycol. Ingestion of the product over the recommended dose by a young child could result in significant toxicity and could potentially be lethal.

Treatment of overdose with NORVIR consists of general supportive measures including monitoring of vital signs and observation of the clinical status of the patient. There is no specific antidote for overdose with NORVIR. If indicated, elimination of unabsorbed drug should be achieved by gastric lavage; usual precautions should be observed to maintain the airway. Administration of activated charcoal may also be used to aid in removal of unabsorbed drug. Since ritonavir is extensively metabolized by the liver and is highly protein bound, dialysis is unlikely to be beneficial in significant removal of the drug. However, dialysis can remove both alcohol and propylene glycol in the case of overdose with ritonavir oral solution. A Certified Poison Control Center should be consulted for up-to-date information on the management of overdose with NORVIR.

11 DESCRIPTION

NORVIR (ritonavir) is an inhibitor of HIV protease with activity against the Human Immunodeficiency Virus (HIV).

Ritonavir is chemically designated as 10-Hydroxy-2-methyl-5-(1-methylethyl)-1- [2-(1-methylethyl)-4-thiazolyl]-3,6-dioxo-8,11-bis(phenylmethyl)-2,4,7,12- tetraazatridecan-13-oic acid, 5-thiazolylmethyl ester, [5S-(5R*,8R*,10R*,11R*)]. Its molecular formula is C37H48N6O5S2, and its molecular weight is 720.95. Ritonavir has the following structural formula:

[norvir chem structure]

Ritonavir is a white-to-light-tan powder. Ritonavir has a bitter metallic taste. It is freely soluble in methanol and ethanol, soluble in isopropanol and practically insoluble in water.

NORVIR tablets are available for oral administration in a strength of 100 mg ritonavir with the following inactive ingredients: copovidone, anhydrous dibasic calcium phosphate, sorbitan monolaurate, colloidal silicon dioxide, and sodium stearyl fumarate. The following are the ingredients in the film coating: hypromellose, titanium dioxide, polyethylene glycol 400, hydroxypropyl cellulose, talc, polyethylene glycol 3350, colloidal silicon dioxide, and polysorbate 80.

NORVIR oral solution is available for oral administration as 80 mg per mL of ritonavir in a peppermint and caramel flavored vehicle. Each 8-ounce bottle contains 19.2 grams of ritonavir. NORVIR oral solution also contains ethanol, water, polyoxyl 35 castor oil, propylene glycol, anhydrous citric acid to adjust pH, saccharin sodium, peppermint oil, creamy caramel flavoring, and FD&C Yellow No. 6.

12 CLINICAL PHARMACOLOGY

12.1 Mechanism of Action

Ritonavir is an antiretroviral drug [see Microbiology (12.4)].

12.3 Pharmacokinetics

The pharmacokinetics of ritonavir have been studied in healthy volunteers and HIV-infected patients (CD4 greater than or equal to 50 cells per μL). See Table 6 for ritonavir pharmacokinetic characteristics.

Absorption

The absolute bioavailability of ritonavir has not been determined. After a 600 mg dose of oral solution, peak concentrations of ritonavir were achieved approximately 2 hours and 4 hours after dosing under fasting and non-fasting (514 KCal; 9% fat, 12% protein, and 79% carbohydrate) conditions, respectively.

NORVIR tablets are not bioequivalent to NORVIR capsules. Under moderate fat conditions (857 kcal; 31% fat, 13% protein, 56% carbohydrates), when a single 100 mg NORVIR dose was administered as a tablet compared with a capsule, AUC(0- ∞) met equivalence criteria but mean Cmax was increased by 26% (92.8% confidence intervals: ↑15 -↑39%).

No information is available comparing NORVIR tablets to NORVIR capsules under fasting conditions.

Effect of Food on Oral Absorption

When the oral solution was given under non-fasting conditions, peak ritonavir concentrations decreased 23% and the extent of absorption decreased 7% relative to fasting conditions. Dilution of the oral solution, within one hour of administration, with 240 mL of chocolate milk, Advera® or Ensure®did not significantly affect the extent and rate of ritonavir absorption. Administration of a single 600 mg dose oral solution under non-fasting conditions yielded mean ± SD areas under the plasma concentration-time curve (AUCs) of 129.0 ± 39.3 mg•h per mL.

A food effect is observed for NORVIR tablets. Food decreased the bioavailability of the ritonavir tablets when a single 100 mg dose of NORVIR was administered. Under high fat conditions (907 kcal; 52% fat, 15% protein, 33% carbohydrates), a 23% decrease in mean AUC(0-∞) [90% confidence intervals: ↓30%-↓15%], and a 23% decrease in mean Cmax [90% confidence intervals: ↓34%-↓11%]) was observed relative to fasting conditions. Under moderate fat conditions, a 21% decrease in mean AUC(0-∞) [90% confidence intervals: ↓28%-↓13%], and a 22% decrease in mean Cmax [90% confidence intervals: ↓33%-↓9%]) was observed relative to fasting conditions.

However, the type of meal administered did not change ritonavir tablet bioavailability when high fat was compared to moderate fat meals.

Metabolism

Nearly all of the plasma radioactivity after a single oral 600 mg dose of 14C-ritonavir oral solution (n = 5) was attributed to unchanged ritonavir. Five ritonavir metabolites have been identified in human urine and feces. The isopropylthiazole oxidation metabolite (M-2) is the major metabolite and has antiviral activity similar to that of parent drug; however, the concentrations of this metabolite in plasma are low. In vitro studies utilizing human liver microsomes have demonstrated that cytochrome P450 3A (CYP3A) is the major isoform involved in ritonavir metabolism, although CYP2D6 also contributes to the formation of M–2.

Elimination

In a study of five subjects receiving a 600 mg dose of 14C-ritonavir oral solution, 11.3 ± 2.8% of the dose was excreted into the urine, with 3.5 ± 1.8% of the dose excreted as unchanged parent drug. In that study, 86.4 ± 2.9% of the dose was excreted in the feces with 33.8 ± 10.8% of the dose excreted as unchanged parent drug. Upon multiple dosing, ritonavir accumulation is less than predicted from a single dose possibly due to a time and dose-related increase in clearance.

Table 6. Ritonavir Pharmacokinetic Characteristics
Parameter N Values (Mean ± SD)
Vβ/F‡ 91 0.41 ± 0.25 L/kg
t½ 3 - 5 h
CL/F SS† 10 8.8 ± 3.2 L/h
CL/F‡ 91 4.6 ± 1.6 L/h
CLR 62 < 0.1 L/h
RBC/Plasma Ratio 0.14
Percent Bound* 98 to 99%
† SS = steady state; patients taking ritonavir 600 mg q12h.
‡ Single ritonavir 600 mg dose.
* Primarily bound to human serum albumin and alpha-1 acid glycoprotein over the ritonavir concentration range of 0.01 to 30 µg/mL.

Effects on Electrocardiogram

QTcF interval was evaluated in a randomized, placebo and active (moxifloxacin 400 mg once-daily) controlled crossover study in 45 healthy adults, with 10 measurements over 12 hours on Day 3. The maximum mean (95% upper confidence bound) time-matched difference in QTcF from placebo after baseline correction was 5.5 (7.6) milliseconds (msec) for 400 mg twice-daily ritonavir. Ritonavir 400 mg twice daily resulted in Day 3 ritonavir exposure that was approximately 1.5 fold higher than observed with ritonavir 600 mg twice-daily dose at steady state.

PR interval prolongation was also noted in subjects receiving ritonavir in the same study on Day 3. The maximum mean (95% confidence interval) difference from placebo in the PR interval after baseline correction was 22 (25) msec for 400 mg twice-daily ritonavir [see Warnings and Precautions (5.6)].

Special Populations

Gender, Race and Age

No age-related pharmacokinetic differences have been observed in adult patients (18 to 63 years). Ritonavir pharmacokinetics have not been studied in older patients.

A study of ritonavir pharmacokinetics in healthy males and females showed no statistically significant differences in the pharmacokinetics of ritonavir. Pharmacokinetic differences due to race have not been identified.

Pediatric Patients

Steady-state pharmacokinetics were evaluated in 37 HIV-infected patients ages 2 to 14 years receiving doses ranging from 250 mg per m2 twice-daily to 400 mg per m2 twice-daily in PACTG Study 310, and in 41 HIV-infected patients ages 1 month to 2 years at doses of 350 and 450 mg per m2 twice-daily in PACTG Study 345. Across dose groups, ritonavir steady-state oral clearance (CL/F/m2) was approximately 1.5 to 1.7 times faster in pediatric patients than in adult subjects. Ritonavir concentrations obtained after 350 to 400 mg per m2 twice-daily in pediatric patients greater than 2 years were comparable to those obtained in adults receiving 600 mg (approximately 330 mg per m2) twice-daily. The following observations were seen regarding ritonavir concentrations after administration with 350 or 450 mg per m2 twice-daily in children less than 2 years of age. Higher ritonavir exposures were not evident with 450 mg per m2 twice-daily compared to the 350 mg per m2twice-daily. Ritonavir trough concentrations were somewhat lower than those obtained in adults receiving 600 mg twice-daily. The area under the ritonavir plasma concentration time curve and trough concentrations obtained after administration with 350 or 450 mg per m2 twice-daily in children less than 2 years were approximately 16% and 60% lower, respectively, than that obtained in adults receiving 600 mg twice daily.

Renal Impairment

Ritonavir pharmacokinetics have not been studied in patients with renal impairment, however, since renal clearance is negligible, a decrease in total body clearance is not expected in patients with renal impairment.

Hepatic Impairment

Dose-normalized steady-state ritonavir concentrations in subjects with mild hepatic impairment (400 mg twice-daily, n = 6) were similar to those in control subjects dosed with 500 mg twice-daily. Dose-normalized steady-state ritonavir exposures in subjects with moderate hepatic impairment (400 mg twice-daily, n= 6) were about 40% lower than those in subjects with normal hepatic function (500 mg twice-daily, n = 6). Protein binding of ritonavir was not statistically significantly affected by mild or moderately impaired hepatic function. No dose adjustment is recommended in patients with mild or moderate hepatic impairment. However, health care providers should be aware of the potential for lower ritonavir concentrations in patients with moderate hepatic impairment and should monitor patient response carefully. Ritonavir has not been studied in patients with severe hepatic impairment.

Pregnancy

Based on evaluation of the published literature, ritonavir exposures are reduced during pregnancy relative to postpartum.

Drug Interactions

[see also Contraindications (4), Warnings and Precautions (5.1), and Drug Interactions (7)]

Table 7 and Table 8 summarize the effects on AUC and Cmax, with 95% confidence intervals (95% CI), of co-administration of ritonavir with a variety of drugs. For information about clinical recommendations see Table 5 in Drug Interactions (7).

Table 7. Drug Interactions - Pharmacokinetic Parameters for Ritonavir in the Presence of the Co-administered Drug
Co-administered Drug Dose of Co-administered Drug (mg) Dose of NORVIR (mg) N AUC % (95% CI) Cmax(95% CI) Cmin (95% CI)
Clarithromycin 500 q12h, 4 d 200 q8h, 4 d 22 ↑ 12% (2, 23%) ↑ 15% (2, 28%) ↑ 14% (-3, 36%)
Didanosine 200 q12h, 4 d 600 q12h, 4 d 12 ↔ ↔ ↔
Fluconazole 400 single dose, day 1; 200 daily, 4 d 200 q6h, 4 d 8 ↑ 12% (5, 20%) ↑ 15% (7, 22%) ↑ 14% (0, 26%)
Fluoxetine 30 q12h, 8 d 600 single dose, 1 d 16 ↑ 19% (7, 34%) ↔ ND
Ketoconazole 200 daily, 7 d 500 q12h, 10 d 12 ↑ 18% (-3, 52%) ↑ 10% (-11, 36%) ND
Rifampin 600 or 300 daily, 10 d 500 q12h, 20 d 7, 9* ↓ 35% (7, 55%) ↓ 25% (-5, 46%) ↓ 49% (-14, 91%)
Voriconazole 400 q12h, 1 d; then 200 q12h, 8 d 400 q12h, 9 d ↔ ↔ ND
Zidovudine 200 q8h, 4 d 300 q6h, 4 d 10 ↔ ↔ ↔

Table 8. Drug Interactions - Pharmacokinetic Parameters for Co-administered Drug in the Presence of NORVIR
Co-administered Drug Dose of Co-administered Drug (mg) Dose of NORVIR (mg) N AUC % (95% CI) Cmax(95% CI) Cmin (95% CI)
Alprazolam 1, single dose 500 q12h, 10 d 12 ↓ 12% (-5, 30%) ↓ 16% (5, 27%) ND
Avanafil 50, single dose 600 q12h 146 ↑ 13-fold ↑ 2.4-fold ND
Clarithromycin
14-OH clarithromycin metabolite 500 q12h, 4 d 200 q8h, 4 d 22 ↑ 77% (56, 103%)
↓ 100% ↑ 31% (15, 51%)
↓ 99% ↑ 2.8-fold (2.4, 3.3X)
↓ 100%
Desipramine
2-OH desipramine metabolite 100, single dose 500 q12h, 12 d 14 ↑ 145% (103, 211%)
↓ 15% (3, 26%) ↑ 22% (12, 35%)
↓ 67% (62, 72%) ND
ND
Didanosine 200 q12h, 4 d 600 q12h, 4 d 12 ↓ 13% (0, 23%) ↓ 16% (5, 26%) ↔
Ethinyl estradiol 50 µg single dose 500 q12h, 16 d 23 ↓ 40% (31, 49%) ↓ 32% (24, 39%) ND
Fluticasone propionate aqueous nasal spray 200 mcg qd, 7 d 100 mg q12h, 7 d 18 ↑ approximately 350-fold5 ↑ approximately 25-fold5
Indinavir1
Day 14
Day 15 400 q12h, 15 d 400 q12h, 15 d 10
↑ 6% (-14, 29%)
↓ 7% (-22, 28%)
↓ 51% (40, 61%)
↓ 62% (52, 70%) ↑ 4-fold (2.8, 6.8X)
↑ 4-fold (2.5, 6.5X)
Ketoconazole 200 daily, 7 d 500 q12h, 10 d 12 ↑ 3.4-fold (2.8, 4.3X) ↑ 55% (40, 72%) ND
Meperidine
Normeperidine metabolite 50 oral single dose 500 q12h, 10 d 8
6 ↓ 62% (59, 65%)
↑ 47% (-24, 345%) ↓ 59% (42, 72%)
↑ 87% (42, 147%) ND
ND
Methadone2 5, single dose 500 q12h, 15 d 11 ↓ 36% (16, 52%) ↓ 38% (28, 46%) ND
Raltegravir 400, single dose 100 q12h, 16 d 10 ↓ 16% (-30, 1%) ↓ 24% (-45, 4%) ↓ 1% (-30, 40%)
Rivaroxaban 10, single dose
(days 0 and 7) 600 q12h
(days 2 to 7) 12 ↑ 150% (130-170%)7 ↑ 60% (40-70%)7 ND
Rifabutin
25-O-desacetyl rifabutin metabolite 150 daily, 16 d 500 q12h, 10 d 5,
11* ↑ 4-fold (2.8, 6.1X)
↑ 38-fold (28, 56X) ↑ 2.5-fold (1.9, 3.4X)
↑ 16-fold (13, 20X) ↑ 6-fold (3.5, 18.3X)
↑ 181-fold (ND)
Sildenafil 100, single dose 500 twice daily, 8 d 28 ↑ 11-fold ↑ 4-fold ND
Simeprevir 200 mg qd, 7 d 100 mg bid,15 d 12 ↑ 618% (463%-815%)8 ↑370% (284%-476%)8 ↑1335% (929%-1901%)8
Sulfamethoxazole3 800, single dose 500 q12h, 12 d 15 ↓ 20% (16, 23%) ↔ ND
Tadalafil 20 mg, single dose 200 mg q12h ↑ 124% ↔ ND
Theophylline 3 mg/kg q8h, 15 d 500 q12h, 10 d 13, 11* ↓ 43% (42, 45%) ↓ 32% (29, 34%) ↓ 57% (55, 59%)
Trazodone 50 mg, single dose 200 mg q12h, 4 doses 10 ↑ 2.4-fold ↑ 34%
Trimethoprim3 160, single dose 500 q12h, 12 d 15 ↑ 20% (3, 43%) ↔ ND
Vardenafil 5 mg 600 q12h ↑ 49-fold ↑ 13-fold ND
Voriconazole 400 q12h, 1 d; then 200 q12h, 8 d 400 q12h, 9 d ↓ 82% ↓ 66%
400 q12h, 1 d; then 200 q12h, 8 d 100 q12h, 9 d ↓ 39% ↓ 24%
Warfarin
S-Warfarin
R-Warfarin 5, single dose 400 q12h, 12d 12 ↑ 9% (-17, 44%)4
↓ 33% (-38, -27%)4 ↓ 9% (-16, -2%)4
↔ ND
ND
Zidovudine 200 q8h, 4 d 300 q6h, 4 d 9 ↓ 25% (15, 34%) ↓ 27% (4, 45%) ND
1 Ritonavir and indinavir were co-administered for 15 days; Day 14 doses were administered after a 15%-fat breakfast (757 Kcal) and 9%-fat evening snack (236 Kcal), and Day 15 doses were administered after a 15%-fat breakfast (757 Kcal) and 32%-fat dinner (815 Kcal). Indinavir Cminwas also increased 4-fold. Effects were assessed relative to an indinavir 800 mg q8h regimen under fasting conditions.
2 Effects were assessed on a dose-normalized comparison to a methadone 20 mg single dose.
3 Sulfamethoxazole and trimethoprim taken as single combination tablet.
4 90% CI presented for R- and S-warfarin AUC and Cmax ratios.
5 This significant increase in plasma fluticasone propionate exposure resulted in a significant decrease (86%) in plasma cortisol AUC.
6 For the reference arm: N=14 for Cmax and AUC(0-inf), and for the test arm: N=13 for Cmax and N=4 for AUC(0-inf).
7 90% CI presented for rivaroxaban
8 90% CI presented for simeprevir (change in exposure presented as percentage increase)
↑ Indicates increase.
↓ Indicates decrease.
↔ Indicates no change.
* Parallel group design; entries are subjects receiving combination and control regimens, respectively.

12.4 Microbiology

Mechanism of Action

Ritonavir is a peptidomimetic inhibitor of the HIV-1 protease. Inhibition of HIV protease renders the enzyme incapable of processing the Gag-Pol polyprotein precursor which leads to production of non-infectious immature HIV particles.

Antiviral Activity in Cell Culture

The activity of ritonavir was assessed in acutely infected lymphoblastoid cell lines and in peripheral blood lymphocytes. The concentration of drug that inhibits 50% (EC50) value of viral replication ranged from 3.8 to 153 nM depending upon the HIV-1 isolate and the cells employed. The average EC50 value for low passage clinical isolates was 22 nM (n = 13). In MT4 cells, ritonavir demonstrated additive effects against HIV-1 in combination with either didanosine (ddI) or zidovudine (ZDV). Studies which measured cytotoxicity of ritonavir on several cell lines showed that greater than 20 microM was required to inhibit cellular growth by 50% resulting in a cell culture therapeutic index of at least 1000.

Resistance

HIV-1 isolates with reduced susceptibility to ritonavir have been selected in cell culture. Genotypic analysis of these isolates showed mutations in the HIV-1 protease gene leading to amino acid substitutions I84V, V82F, A71V, and M46I. Phenotypic (n = 18) and genotypic (n = 48) changes in HIV-1 isolates from selected patients treated with ritonavir were monitored in phase I/II trials over a period of 3 to 32 weeks. Substitutions associated with the HIV–1 viral protease in isolates obtained from 43 patients appeared to occur in a stepwise and ordered fashion at positions V82A/F/T/S, I54V, A71V/T, and I36L, followed by combinations of substitutions at an additional 5 specific amino acid positions (M46I/L, K20R, I84V, L33F and L90M). Of 18 patients for whom both phenotypic and genotypic analysis were performed on free virus isolated from plasma, 12 showed reduced susceptibility to ritonavir in cell culture. All 18 patients possessed one or more substitutions in the viral protease gene. The V82A/F substitution appeared to be necessary but not sufficient to confer phenotypic resistance. Phenotypic resistance was defined as a greater than or equal to 5-fold decrease in viral sensitivity in cell culture from baseline.

Cross-Resistance to Other Antiretrovirals

Among protease inhibitors variable cross-resistance has been recognized. Serial HIV-1 isolates obtained from six patients during ritonavir therapy showed a decrease in ritonavir susceptibility in cell culture but did not demonstrate a concordant decrease in susceptibility to saquinavir in cell culture when compared to matched baseline isolates. However, isolates from two of these patients demonstrated decreased susceptibility to indinavir in cell culture (8-fold). Isolates from 5 patients were also tested for cross-resistance to amprenavir and nelfinavir; isolates from 3 patients had a decrease in susceptibility to nelfinavir (6- to 14-fold), and none to amprenavir. Cross-resistance between ritonavir and reverse transcriptase inhibitors is unlikely because of the different enzyme targets involved. One ZDV-resistant HIV-1 isolate tested in cell culture retained full susceptibility to ritonavir.

13 NONCLINICAL TOXICOLOGY

13.1 Carcinogenesis, Mutagenesis, Impairment of Fertility

Carcinogenesis

Carcinogenicity studies in mice and rats have been carried out on ritonavir. In male mice, at levels of 50, 100 or 200 mg per kg per day, there was a dose dependent increase in the incidence of both adenomas and combined adenomas and carcinomas in the liver. Based on AUC measurements, the exposure at the high dose was approximately 0.3-fold for males that of the exposure in humans with the recommended therapeutic dose (600 mg twice-daily). There were no carcinogenic effects seen in females at the dosages tested. The exposure at the high dose was approximately 0.6-fold for the females that of the exposure in humans. In rats dosed at levels of 7, 15 or 30 mg per kg per day there were no carcinogenic effects. In this study, the exposure at the high dose was approximately 6% that of the exposure in humans with the recommended therapeutic dose. Based on the exposures achieved in the animal studies, the significance of the observed effects is not known.

Mutagenesis

However, ritonavir was found to be negative for mutagenic or clastogenic activity in a battery of in in vitro and in vivo assays including the Ames bacterial reverse mutation assay using S. typhimurium and E. coli, the mouse lymphoma assay, the mouse micronucleus test and chromosomal aberration assays in human lymphocytes.

Impairment of Fertility

Ritonavir produced no effects on fertility in rats at drug exposures approximately 40% (male) and 60% (female) of that achieved with the proposed therapeutic dose. Higher dosages were not feasible due to hepatic toxicity.

14 CLINICAL STUDIES

The activity of NORVIR as monotherapy or in combination with nucleoside reverse transcriptase inhibitors has been evaluated in 1446 patients enrolled in two double-blind, randomized trials.

14.1 Advanced Patients with Prior Antiretroviral Therapy

Study 247 was a randomized, double-blind trial (with open-label follow-up) conducted in HIV-infected patients with at least nine months of prior antiretroviral therapy and baseline CD4 cell counts less than or equal to 100 cells per μL. NORVIR 600 mg twice-daily or placebo was added to each patient's baseline antiretroviral therapy regimen, which could have consisted of up to two approved antiretroviral agents. The study accrued 1,090 patients, with mean baseline CD4 cell count at study entry of 32 cells per μL. After the clinical benefit of NORVIR therapy was demonstrated, all patients were eligible to switch to open-label NORVIR for the duration of the follow-up period. Median duration of double-blind therapy with NORVIR and placebo was 6 months. The median duration of follow-up through the end of the open-label phase was 13.5 months for patients randomized to NORVIR and 14 months for patients randomized to placebo.

The cumulative incidence of clinical disease progression or death during the double-blind phase of Study 247 was 26% for patients initially randomized to NORVIR compared to 42% for patients initially randomized to placebo. This difference in rates was statistically significant.

Cumulative mortality through the end of the open-label follow-up phase for patients enrolled in Study 247 was 18% (99/543) for patients initially randomized to NORVIR compared to 26% (142/547) for patients initially randomized to placebo. This difference in rates was statistically significant. However, since the analysis at the end of the open-label phase includes patients in the placebo arm who were switched from placebo to NORVIR therapy, the survival benefit of NORVIR cannot be precisely estimated.

During the double-blind phase of Study 247, CD4 cell counts increases from baseline for patients randomized to NORVIR at Week 2 and Week 4 were observed. From Week 4 and through Week 24, mean CD4 cell counts for patients randomized to NORVIR appeared to plateau. In contrast, there was no apparent change in mean CD4 cell counts for patients randomized to placebo at any visit between baseline and Week 24 of the double-blind phase of Study 247.

14.2 Patients without Prior Antiretroviral Therapy

In Study 245, 356 antiretroviral-naive HIV-infected patients (mean baseline CD4 = 364 cells per μL) were randomized to receive either NORVIR 600 mg twice-daily, zidovudine 200 mg three-times-daily, or a combination of these drugs.

During the double-blind phase of study 245, greater mean CD4 cell count increases were observed from baseline to Week 12 in the NORVIR-containing arms compared to the zidovudine arms. Mean CD4 cell count changes subsequently appeared to plateau through Week 24 in the NORVIR arm, whereas mean CD4 cell counts gradually diminished through Week 24 in the zidovudine and NORVIR plus zidovudine arms.

Greater mean reductions in plasma HIV-1 RNA levels were observed from baseline to Week 2 for the NORVIR-containing arms compared to the zidovudine arm. After Week 2 and through Week 24, mean plasma HIV-1 RNA levels either remained stable in the NORVIR and zidovudine arms or gradually rebounded toward baseline in the NORVIR plus zidovudine arm.

15 REFERENCES

Sewester CS. Calculations. In: Drug Facts and Comparisons. St. Louis, MO: J.B. Lippincott Co; January, 1997:xix.

16 HOW SUPPLIED/STORAGE AND HANDLING

NORVIR (ritonavir) tablets and NORVIR (ritonavir) oral solution are available in the following strengths and package sizes:

16.1 NORVIR Tablets, 100 mg Ritonavir

NORVIR (ritonavir) tablets are white film-coated ovaloid tablets debossed with the "a" logo and the code NK.

Bottles of 30 tablets each (NDC 0074-3333-30).

Recommended Storage

Store at or below 30°C (86°F). Exposure to temperatures up to 50°C (122°F) for seven days permitted. Dispense in original container or USP equivalent tight container (60 mL or less). For patient use: exposure of this product to high humidity outside the original or USP equivalent tight container (60 mL or less) for longer than 2 weeks is not recommended.

16.2 NORVIR Oral Solution, 80 mg per mL Ritonavir

NORVIR (ritonavir) oral solution is an orange-colored liquid, supplied in amber-colored, multi-dose bottles containing 600 mg ritonavir per 7.5 mL marked dosage cup (80 mg per mL).

240 mL bottles (NDC 0074-1940-63).

Recommended Storage

Store NORVIR oral solution at room temperature 20°-25°C (68°-77°F). Do not refrigerate. Shake well before each use. Use by product expiration date.

Product should be stored and dispensed in the original container.

Avoid exposure to excessive heat. Keep cap tightly closed.

17 PATIENT COUNSELING INFORMATION

Advise the patient to read the FDA-approved patient labeling (Patient Information)

Patients or parents of patients should be informed that:

General Information

 They should pay special attention to accurate administration of their dose to minimize the risk of accidental overdose or underdose of NORVIR.

 They should inform their healthcare provider if their children’s weight changes in order to make sure that the child’s NORVIR dose is the correct one.

 Take NORVIR with meals.

 For adult patients taking NORVIR tablets, the maximum dose of 600 mg twice daily by mouth with meals should not be exceeded.

 Advise pregnant women that use of NORVIR oral solution during pregnancy is not recommended due to its alcohol content [see Dosage and Administration (2.1) and Use in Specific Population (8.1)].

 Patients should remain under the care of a physician while using NORVIR. Patients should be advised to take NORVIR and other concomitant antiretroviral therapy every day as prescribed. NORVIR must always be used in combination with other antiretroviral drugs. Patients should not alter the dose or discontinue therapy without consulting with their doctor. If a dose of NORVIR is missed patients should take the dose as soon as possible and then return to their normal schedule. However, if a dose is skipped the patient should not double the next dose.

 NORVIR is not a cure for HIV-1 infection and patients may continue to experience illnesses associated with HIV-1 infection, including opportunistic infections. Patients should remain under the care of a physician when using NORVIR.
Patients should be advised to avoid doing things that can spread HIV-1 infection to others.

Do not share needles or other injection equipment.
Do not share personal items that can have blood or body fluids on them, like toothbrushes and razor blades.
Do not have any kind of sex without protection. Always practice safe sex by using a latex or polyurethane condom to lower the chance of sexual contact with semen, vaginal secretions, or blood.
Do not breastfeed. Instruct women with HIV-1 infection not breastfeed because HIV-1 can be passed to the infant in the breast milk [see Use in Specific Populations (8.2)].

 Sustained decreases in plasma HIV-1 RNA have been associated with a reduced risk of progression to AIDS and death.

Drug Interactions

 NORVIR may interact with some drugs; therefore, patients should be advised to report to their doctor the use of any other prescription, non-prescription medication or herbal products, particularly St. John's Wort.

 Instruct patients receiving combined hormonal contraception to use an effective alternative contraceptive method or an additional barrier method during therapy with NORVIR because hormonal levels may decrease [see Drug Interactions (7.3), Use in Specific Populations (8.3)].

Potential Adverse Effects

 Pre-existing liver disease including Hepatitis B or C can worsen with use of NORVIR. This can be seen as worsening of transaminase elevations or hepatic decompensation. Patients should be advised that their liver function tests will need to be monitored closely especially during the first several months of NORVIR treatment and that they should notify their healthcare provider if they develop the signs and symptoms of worsening liver disease including loss of appetite, abdominal pain, jaundice, and itchy skin.

 Pancreatitis, including some fatalities, has been observed in patients receiving NORVIR therapy. Your patients should let you know of signs and symptoms (nausea, vomiting, and abdominal pain) that might be suggestive of pancreatitis.

 Skin rashes ranging in severity from mild to Stevens-Johnson syndrome have been reported in patients receiving NORVIR. Patients should be advised to contact their healthcare provider if they develop a rash while taking NORVIR. The healthcare provider will determine if treatment should be continued or an alternative antiretroviral regimen used.

 Pregnancy Exposure Registry

Inform patients that there is an antiretroviral pregnancy registry that monitors fetal outcomes of pregnant women exposed to NORVIR [see Use in Specific Populations (8.1)].

 NORVIR may produce changes in the electrocardiogram (e.g., PR prolongation). Patients should consult their physician if they experience symptoms such as dizziness, lightheadedness, abnormal heart rhythm or loss of consciousness.

 Treatment with NORVIR therapy can result in substantial increases in the concentration of total cholesterol and triglycerides.

 New onset of diabetes or exacerbation of pre-existing diabetes mellitus, and hyperglycemia have been reported. Patients should be advised to notify their healthcare provider if they develop the signs and symptoms of diabetes mellitus including frequent urination, excessive thirst, extreme hunger or unusual weight loss and/or an increased blood sugar while on NORVIR as they may require a change in their diabetes treatment or new treatment.

 Immune reconstitution syndrome has been reported in HIV-infected patients treated with combination antiretroviral therapy, including NORVIR.

 Redistribution or accumulation of body fat may occur in patients receiving antiretroviral therapy and that the cause and long term health effects of these conditions are not known at this time.

 Patients with hemophilia may experience increased bleeding when treated with protease inhibitors such as NORVIR.

 If they are receiving avanafil, sildenafil, tadalafil, or vardenafil for the treatment of erectile dysfunction, they may be at an increased risk of associated adverse reactions including hypotension, visual changes, and sustained erection, and should promptly report any symptoms to their doctor. They should seek medical assistance immediately if they develop a sustained penile erection lasting more than 4 hours while taking NORVIR and a PDE 5 Inhibitor such as Stendra®, Viagra®, Cialis® or Levitra®. If they are currently using or planning to use avanafil or tadalafil (for the treatment of pulmonary arterial hypertension) they should ask their doctor about potential adverse reactions these medications may cause when taken with NORVIR. The doctor may choose not to keep them on avanafil, or may adjust the dose of tadalafil while initiating treatment with NORVIR. Concomitant use of Revatio® (sildenafil) with NORVIR is contraindicated in patients with pulmonary arterial hypertension (PAH).

 Continued NORVIR therapy at a dose of 600 mg twice daily following loss of viral suppression may increase the likelihood of cross-resistance to other protease inhibitors.

NORVIR tablets and oral solution are manufactured by:

AbbVie Inc.

North Chicago, IL 60064 USA

© 2016 AbbVie Inc. All rights reserved.

03-B455

PATIENT PACKAGE INSERT

Patient Information

NORVIR® (NOR-VEER)

(ritonavir)

Tablet

NORVIR® (NOR-VEER)

(ritonavir)

Oral Solution

Read this Patient Information before you start taking NORVIR and each time you get a refill. There may be new information. This information does not take the place of talking to your doctor about your medical condition or your treatment.

What is the most important information I should know about NORVIR?

NORVIR can interact with other medicines and cause serious side effects. It is important to know the medicines that should not be taken with NORVIR. See the section “Who should not take NORVIR?”

What is NORVIR?

NORVIR is a prescription anti-HIV medicine used with other anti-HIV medicines to treat people with human immunodeficiency virus (HIV) infection. NORVIR is a type of anti-HIV medicine called a protease inhibitor. HIV is the virus that causes AIDS (Acquired Immune Deficiency Syndrome).

When used with other HIV medicines, NORVIR may reduce the amount of HIV in your blood (called “viral load”). NORVIR may also help to increase the number of CD4 (T) cells in your blood which help fight off other infections. Reducing the amount of HIV and increasing the CD4 (T) cell count may improve your immune system. This may reduce your risk of death or infections that can happen when your immune system is weak (opportunistic infections). Patients who took NORVIR in clinical studies had significant reductions in both death and AIDS defining diseases; however NORVIR may not have these effects in all patients.

NORVIR does not cure HIV infection or AIDS and you may continue to experience illnesses associated with HIV-1 infection, including opportunistic infections. You should remain under the care of a doctor when using NORVIR.

Avoid doing things that can spread HIV-1 infection.

Do not share needles or other injection equipment.
Do not share personal items that can have blood or body fluids on them, like toothbrushes and razor blades.
Do not have any kind of sex without protection. Always practice safe sex by using a latex or polyurethane condom to lower the chance of sexual contact with semen, vaginal secretions, or blood.

Who should not take NORVIR?

Do not take NORVIR if you are allergic to ritonavir or any of the ingredients in NORVIR. See the end of this leaflet for a complete list of ingredients in NORVIR.

Do not take NORVIR with any of the following medicines:

alfuzosin (Uroxatral)
amiodarone (Cordarone, Nexterone, Pacerone), dronedarone (Multaq), flecainide (Tambocor), propafenone (Rythmol) or quinidine (Nuedext, Quinaglute, Cardioquin, Quinidex, and others)
colchicine (Colcrys, Col-Probenecid, Probenecid and Colchine), if you have kidney and/or liver problems
voriconazole (VFend) if NORVIR dose is 400 mg every 12 hours or greater
dihydroergotamine (D.H.E. 45, Embolex, Migranal), ergotamine (Cafergot, Ergomar) methylergonovine (Methergine)
cisapride (Propulsid)
St. John’s Wort (Hypericum perforatum)
the cholesterol lowering medicines lovastatin (Mevacor, Altoprev, Advicor) or simvastatin (Zocor, Simcor, Vytorin)
lurasidone (Latuda), pimozide (Orap)
sildenafil (Revatio) only when used for the treatment of pulmonary arterial hypertension
oral midazolam or triazolam (Halcion)

Serious problems can happen if you or your child takes any of these medicines with NORVIR.

What should I tell my doctor before taking NORVIR?

Before taking NORVIR, tell your doctor if you:

have liver problems, including Hepatitis B or Hepatitis C.
have heart problems.
have high blood sugar (diabetes).
have bleeding problems or hemophilia.
are pregnant or plan to become pregnant.

Pregnancy Registry: There is a pregnancy registry for women who take antiviral medicines during pregnancy. The purpose of the registry is to collect information about the health of you and your baby. Talk to your doctor about how you can take part in this registry.

are breastfeeding. Do not breastfeed if you take NORVIR

You should not breastfeed if you have HIV-1 because of the risk of passing HIV-1 to your baby.
It is not known if NORVIR passes into your breast milk.
Talk to your doctor about the best way to feed your baby.

Tell your doctor about all the medicines you take including prescription and nonprescription medicines, vitamins, and herbal supplements. Taking NORVIR and certain other medicines may affect each other causing serious side effects. NORVIR may affect the way other medicines work and other medicines may affect how NORVIR works.

Especially tell your doctor if you take:

medicine to treat HIV
estrogen-based contraceptives (birth control). NORVIR might reduce the effectiveness of estrogen-based contraceptives. You must take additional precautions for birth control such as a condom.
medicine for pain such as tramadol (Ryzolt, Ultracet, Conzip, Ultram), propoxyphene, or meperidine (Demerol)
medicine to treat alcohol abuse such as disulfiram (Antabuse)
medicine for your heart such as disopyramide (Norpace), lidocaine (Xylocaine Viscous), mexiletine, digoxin (Lanoxin), nifedipine (Procardia, Adalat, Afeditab CR), diltiazem (Cardizem, Dilacor, Cartia, Diltzac, Dilt, Taztia, Tiazac) or verapamil (Calan, Covera, Isoptin, Tarka, Verelan)
medicines for panic disorder or anxiety such as buspirone, clorazepate, diazepam, estazolam, flurazepam, and zolpidem
medicine for cancer such as dasatinib (Sprycel), nilotinib (Tasigna) vincristine, or vinblastine
warfarin (Coumadin, Jantoven), rivaroxaban (Xarelto)
medicine for seizures such as carbamazepine (Carbatrol, Equetro, Tegretol, Epitol), clonazepam (Klonopin), ethosuximide (Zarontin, Ethosuximide), divalproex (Depakote, Divalproex Sodium), lamotrigine (Lamictal) or phenytoin (Dilantin, Phenytek)
medicine for depression such as nefazodone, bupropion (Wellbutrin, Aplenzin, Zyban), desipramine (Norpramin) or trazadone, fluoxetine (Prozac), paroxetine (Paxil), amitriptyline, or nortriptyline
medicine for nausea and vomiting such as dronabinol (Marinol) or perphenazine
medicine for fungal infections such as ketoconazole (Nizoral), itraconazole (Sporanox, Onmel) or voriconazole (VFend)
colchicine (Colcrys, Col-Probenecid, Probenecid and Colchine)
medicine for infections such as clarithromycin (Prevpac, Biaxin), rifabutin (Mycobutin), rifampin (Rimactane, Rifadin, Rifater, Rifamate), atovaquone (Mepron, Malarone), bedaquiline (Sirturo), quinine (Qualaquin) or metronidazole (Flagyl, Helidac, Metrocream)
medicine used to treat blood pressure, a heart attack, heart failure, or to lower pressure in the eye such as metoprolol (Lopressor, Toprol-XL), timolol (Cosopt, Betimol, Timoptic, Isatolol, Combigan)
medicine for lung disease such as theophylline and salmeterol (Serevent)
bosentan (Tracleer)
medicine to treat Hepatitis C such as simeprevir (Olysio)
medicine to prevent organ transplant failure such as cyclosporine (Gengraf, Sandimmune, Neoral), tacrolimus (Prograf,) sirolimus (Rapamune)
steroids such as dexamethasone, fluticasone (Advair Diskus, Veramyst, Flovent, Flonase), budesonide (Entocort EC, Pulmicort, Rhinocort), or prednisone
a narcotic medicine such as methadone (Methadose, Dolophine Hydrochloride) or fentanyl (Abstral, Actiq, Fentora, Lazanda, Onsolis, Duragesic)
medicine to treat schizophrenia such as risperidone (Risperdal) or thioridazine
medicine to treat psychosis such as quetiapine (Seroquel)
medicine to treat erectile dysfunction or pulmonary hypertension such as avanafil (Stendra), sildenafil (Viagra, Revatio), vardenafil (Levitra, Staxyn), tadalafil (Cialis, Adcirca). If you are taking avanafil (Stendra), your doctor may need to change it to a different medicine.
midazolam by injection
methamphetamine (Desoxyn)
cholesterol lowering medicine such as atorvastatin (Lipitor) or rosuvastatin (Crestor)

This is not a complete list of medicines that you should tell your doctor that you are taking. Ask your doctor, provider or pharmacist if you are not sure if your medicine is one that is listed above.

Know the medicines you take. Keep a list of them to show your doctor or pharmacist when you get a new medicine. Do not start any new medicines while you are taking NORVIR without first talking with your doctor.

How should I take NORVIR?

Take NORVIR exactly as prescribed by your doctor.
You should stay under a doctor's care when taking NORVIR. Do not change your dose of NORVIR or stop your treatment without talking with your doctor first.
If your child is taking NORVIR, your child’s doctor will decide the right dose based on your child's height and weight. Tell your doctor if your child’s weight changes. Your child should take NORVIR with food. If your child does not tolerate NORVIR Oral Solution, ask your child’s doctor for advice.
Swallow NORVIR tablets whole. Do not chew, break, or crush tablets before swallowing. If you cannot swallow NORVIR tablets whole, tell your doctor. You may need a different medicine.
Take NORVIR with meals.
NORVIR Oral Solution is peppermint or caramel flavored. You can take it alone, or may improve the taste by mixing it with 8 ounces of chocolate milk, Ensure®, or Advera®. NORVIR Oral Solution should be taken within 1 hour if mixed with these fluids. Ask your doctor, nurse or pharmacist about other ways to improve the taste of NORVIR Oral Solution.
Do not run out of NORVIR. Get your NORVIR prescription refilled from you doctor or pharmacy before you run out.
If you miss a dose of NORVIR, take it as soon as possible and then take your next scheduled dose at its regular time. If it is almost time for your next dose, wait and take the next dose at the regular time. Do not double the next dose.
If you take too much NORVIR, call your local poison control center or go to the nearest hospital emergency room right away.

What are the possible side effects of NORVIR?

NORVIR can cause serious side effects including:

See “What is the most important information I should know about NORVIR?”
Liver disease. Some people taking NORVIR in combination with other anti-HIV medicines have developed liver problems which may be life-threatening. Your doctor should do regular blood tests during your combination treatment with NORVIR. If you have chronic hepatitis B or C infection, your doctor should check your blood tests more often because you have an increased chance of developing liver problems. Tell your doctor if you have any of the below signs and symptoms of liver problems:

loss of appetite
pain or tenderness on your right side below your ribs
yellowing of your skin or whites of your eyes
itchy skin

Swelling of your pancreas (Pancreatitis). NORVIR can cause serious pancreas problems, which may lead to death. Tell your doctor right away if you have signs or symptoms of pancreatitis such as:

nausea
vomiting
stomach (abdomen) pain

Allergic Reactions. Sometimes these allergic reactions can become severe and require treatment in a hospital. You should call your doctor right away if you develop a rash. Stop taking NORVIR and get medical help right away if you have any of the following symptoms of a severe allergic reaction:

trouble breathing
wheezing
dizziness or fainting
throat tightness or hoarseness
fast heartbeat or pounding in your chest (tachycardia)
sweating
swelling of your face, lips or tongue
muscle or joint pain
blisters or skin lesions
mouth sores or ulcers

Changes in the electrical activity of your heart called PR prolongation. PR prolongation can cause irregular heartbeats. Tell your doctor right away if you have symptoms such as:

dizziness
lightheadedness
feel faint or pass out
abnormal heart beat

Increase in cholesterol and triglyceride levels. Treatment with NORVIR may increase your blood levels of cholesterol and triglycerides. Your doctor should do blood tests before you start your treatment with NORVIR and regularly to check for an increase in your cholesterol and triglycerides levels.
Diabetes and high blood sugar (hyperglycemia). Some people who take protease inhibitors including NORVIR can get high blood sugar, develop diabetes, or your diabetes can get worse. Tell your doctor if you notice an increase in thirst or urinate often while taking NORVIR.
Changes in your immune system (Immune reconstitution syndrome) can happen when you start taking HIV medicines. Your immune system may get stronger and begin to fight infections that have been hidden in your body for a long time. Call your doctor right away if you start having new symptoms after starting your HIV medicine.
Change in body fat. These changes can happen in people who take antiretroviral therapy. The changes may include an increase amount of fat in the upper back and neck (“buffalo hump”), breast, and around the back and stomach area. Loss of fat from the legs, arms, and face may also happen. The exact cause and long-term health effects of these conditions are not known.
Increased bleeding for hemophiliacs. Some people with hemophilia have increased bleeding with protease inhibitors including NORVIR.

The most common side effects of NORVIR include:

diarrhea
nausea
vomiting
upper and lower stomach (abdomen) pain
tingling feeling or numbness in hands or feet or around the lips
rash
feeling weak or tired

NORVIR liquid contains a large amount of alcohol. If a toddler or young child accidentally drinks more than the recommended dose of NORVIR, it could make him/her sick from too much alcohol. Contact your local poison control center or emergency room immediately if this happens.

Tell your doctor if you have any side effect that bothers you or that does not go away.
These are not all of the possible side effects of NORVIR. For more information, ask your doctor or pharmacist.
Call your doctor for medical advice about side effects. You may report side effects to FDA at 1-800-FDA-1088.

How should I store NORVIR?

Store NORVIR Oral Solution at room temperature between 68°F to 77°F (20°C to 25°C).
Store NORVIR tablets below 30°C (86°F). Exposure to temperatures up to 50°C (122°F) for seven days permitted.
Do not refrigerate NORVIR Oral Solution.
Shake NORVIR Oral Solution well before each use.
Keep NORVIR Oral Solution away from heat.
Store NORVIR tablets and NORVIR oral solution in the original container given to you by the pharmacist.
Exposure of NORVIR tablets to high humidity outside the original container for longer than 2 weeks is not recommended.
Use NORVIR tablets and NORVIR Oral Solution by the expiration date on the bottle.

Keep NORVIR and all medicines out of the reach of children.

General information about NORVIR

Medicines are sometimes prescribed for purposes other than those listed in a Patient Information Leaflet. Do not use this medicine for a condition for which it was not prescribed. Do not share this medicine with other people.

This leaflet summarizes the most important information about NORVIR. If you would like more information, talk to your doctor. You can ask your doctor or pharmacist for information about NORVIR that is written for healthcare professionals.

For more information, call 1-800-633-9110.

What are the ingredients in NORVIR?

Active ingredient: ritonavir

Inactive ingredients:

NORVIR Tablet: copovidone, anhydrous dibasic calcium phosphate, sorbitan monolaurate, colloidal silicon dioxide, and sodium stearyl fumarate. The film coating contains: hypromellose, titanium dioxide, polyethylene glycol 400, hydroxypropyl cellulose, talc, polyethylene glycol 3350, colloidal silicon dioxide, and polysorbate 80.

NORVIR Oral Solution: ethanol, water, polyoxyl 35 castor oil, propylene glycol, anhydrous citric acid to adjust pH, saccharin sodium, peppermint oil, creamy caramel flavoring, and FD&C Yellow No. 6.

This Patient Information has been approved by the U.S. Food and Drug Administration.

NORVIR tablets and oral solution are manufactured by:

AbbVie Inc.
North Chicago, IL 60064 USA

Revised: December 2016

The brands listed are trademarks of their respective owners and are not trademarks of AbbVie Inc. The makers of these brands are not affiliated with and do not endorse AbbVie Inc. or its products.

© 2016 AbbVie Inc. All rights reserved.

SPL UNCLASSIFIED SECTION

03-B455